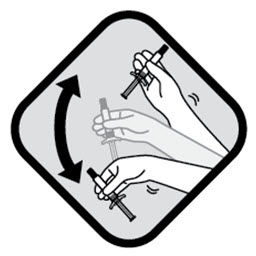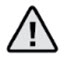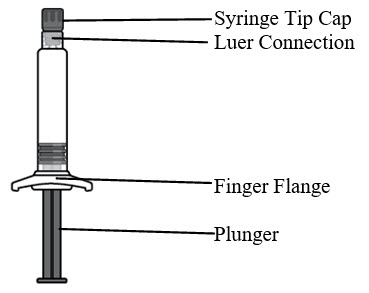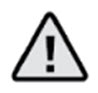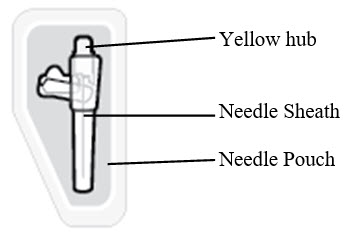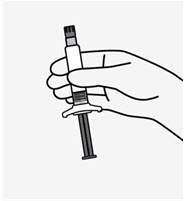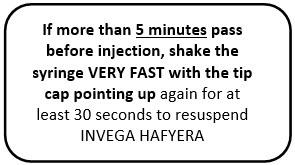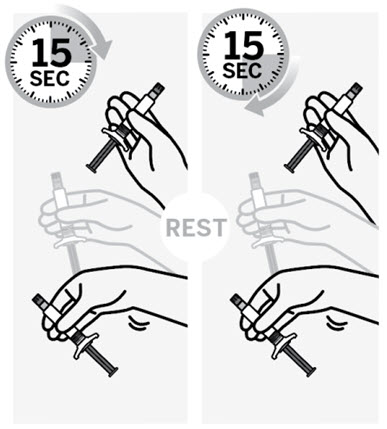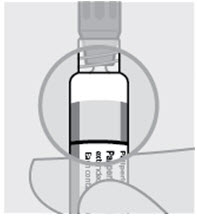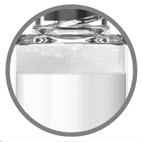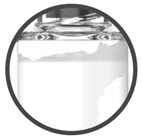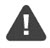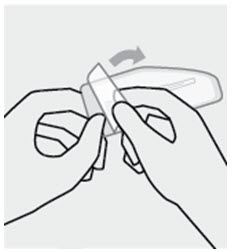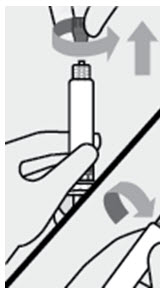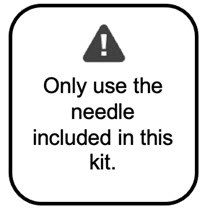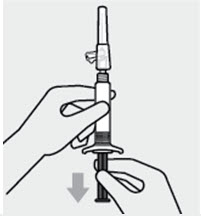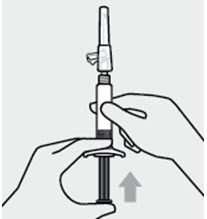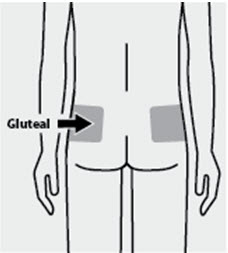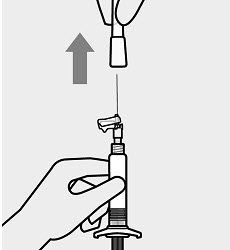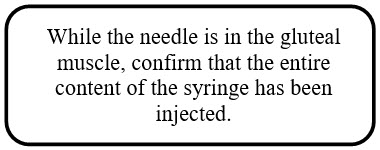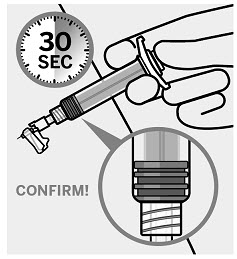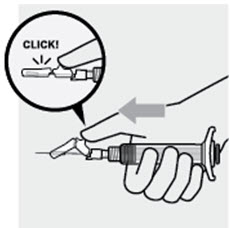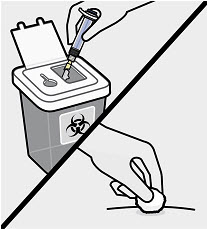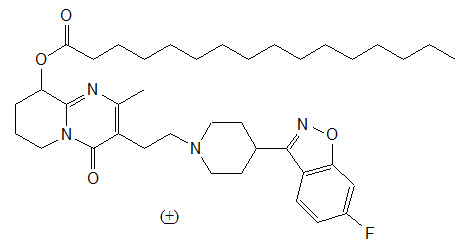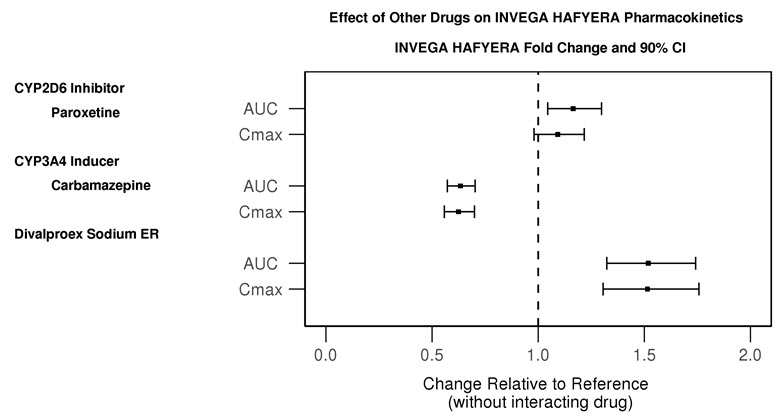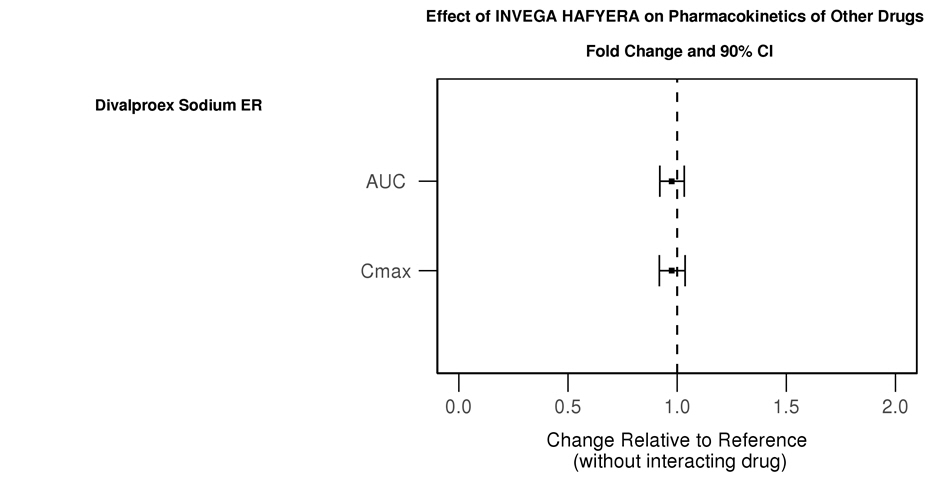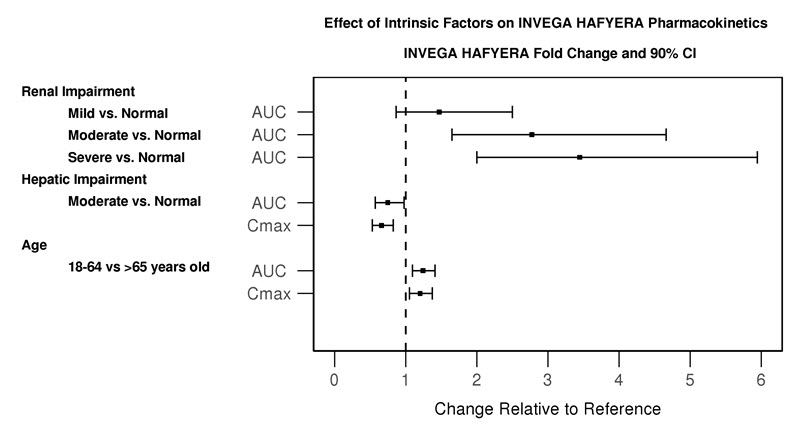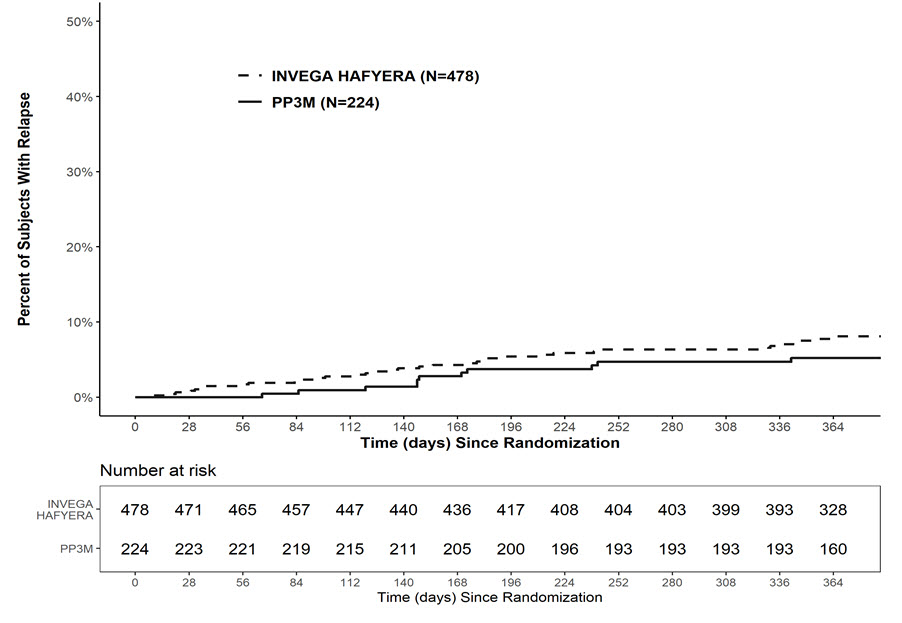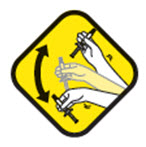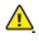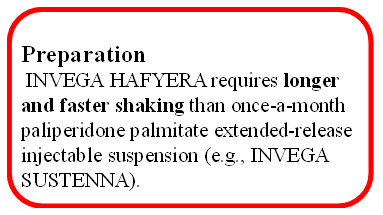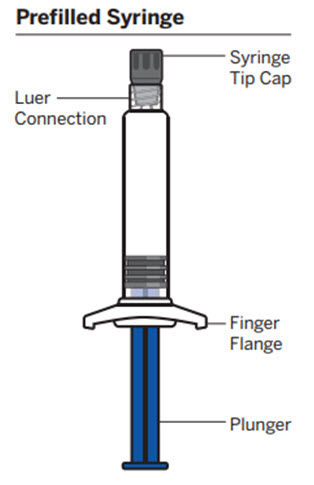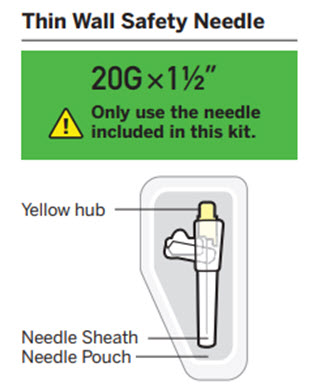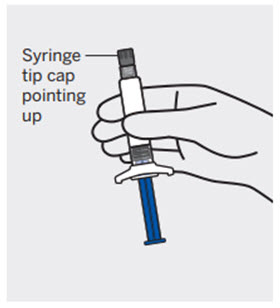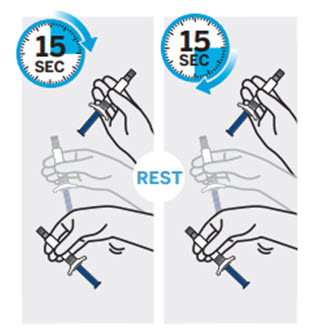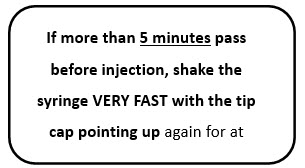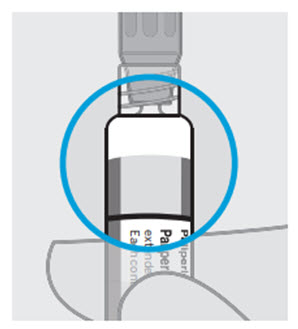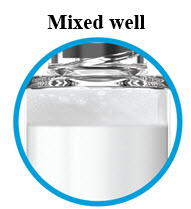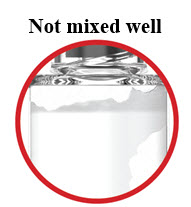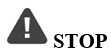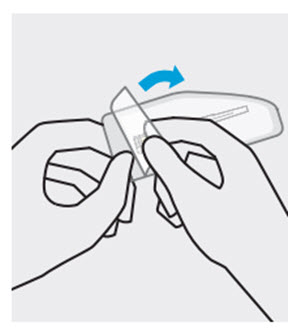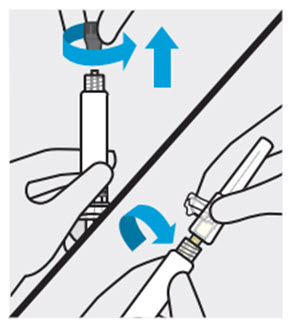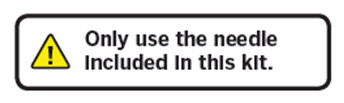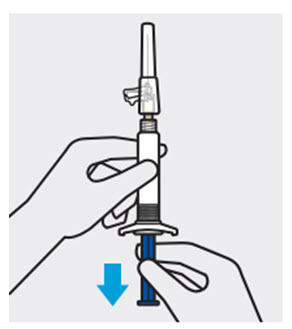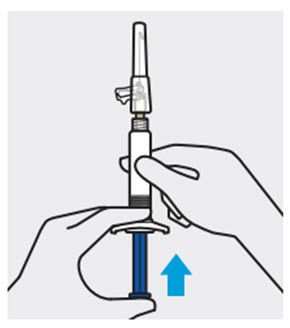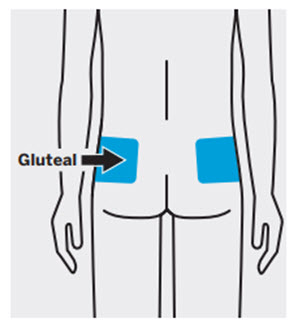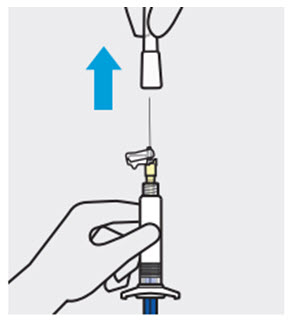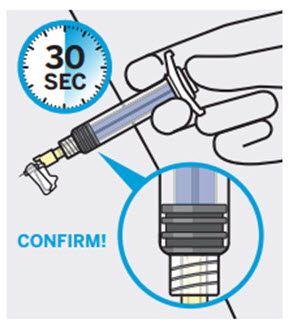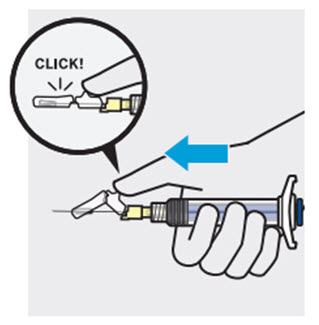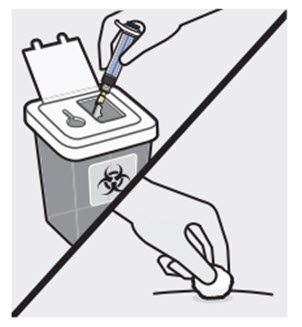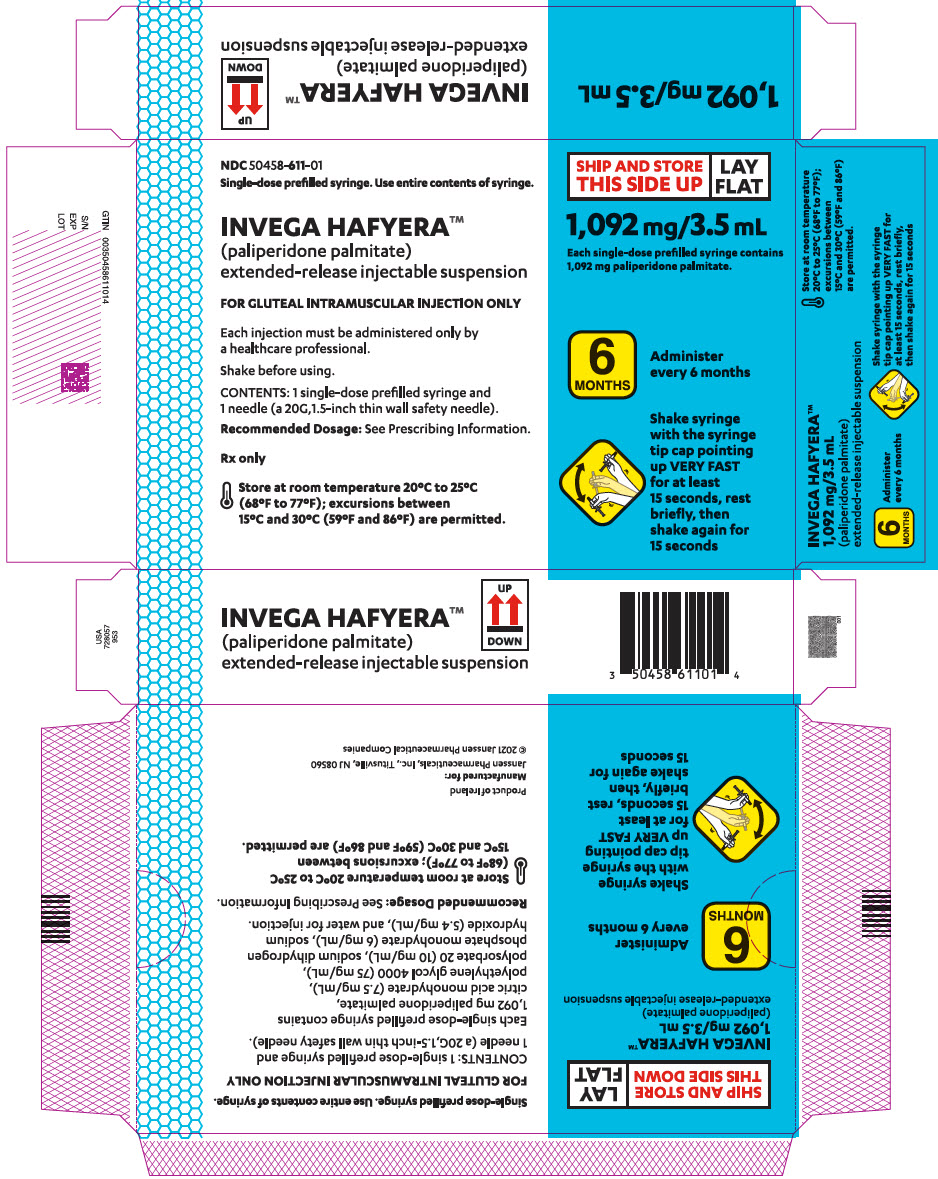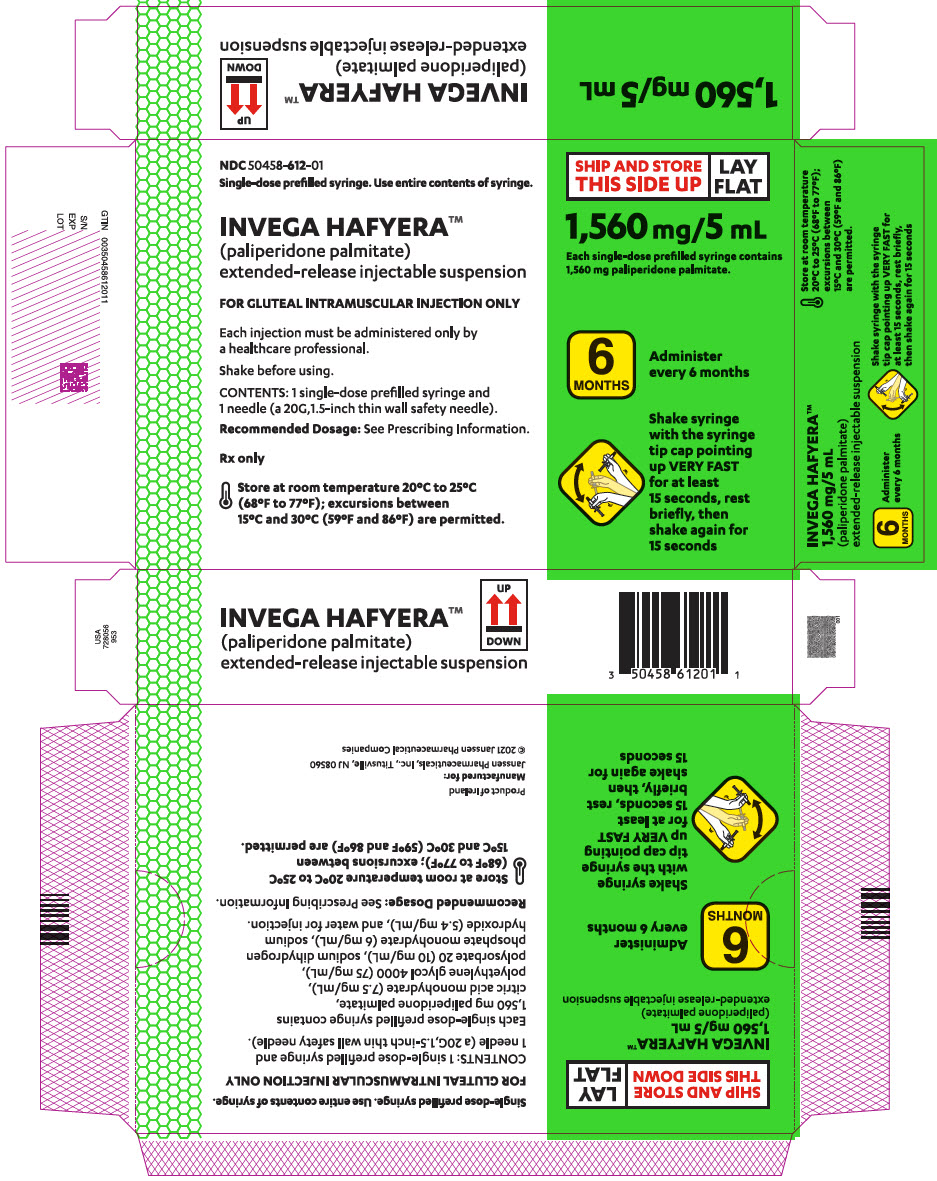 DRUG LABEL: INVEGA HAFYERA
NDC: 50458-611 | Form: INJECTION, SUSPENSION, EXTENDED RELEASE
Manufacturer: Janssen Pharmaceuticals, Inc
Category: prescription | Type: HUMAN PRESCRIPTION DRUG LABEL
Date: 20250218

ACTIVE INGREDIENTS: PALIPERIDONE PALMITATE 1092 mg/3.5 mL
INACTIVE INGREDIENTS: CITRIC ACID MONOHYDRATE; POLYETHYLENE GLYCOL 4000; SODIUM PHOSPHATE, MONOBASIC, MONOHYDRATE; SODIUM HYDROXIDE; WATER

HIGHLIGHTS OF PRESCRIBING INFORMATION

These highlights do not include all the information needed to use INVEGA HAFYERA safely and effectively. See full prescribing information for INVEGA HAFYERA.
INVEGA HAFYERA® (paliperidone palmitate) extended-release injectable suspension, for gluteal intramuscular use
Initial U.S. Approval: 2006

WARNING: INCREASED MORTALITY IN ELDERLY PATIENTS WITH DEMENTIA-RELATED PSYCHOSIS

See full prescribing information for complete boxed warning.

Elderly patients with dementia-related psychosis treated with antipsychotic drugs are at an increased risk of death. INVEGA HAFYERA is not approved for use in patients with dementia-related psychosis. (5.1)

RECENT MAJOR CHANGES

Dosage and Administration (2.4, 2.5) | 9/2024
Warnings and Precautions (5.10) | 1/2025

1 INDICATIONS AND USAGE

INVEGA HAFYERA, an every-six-month injection, is an atypical antipsychotic indicated for the treatment of schizophrenia in adults after they have been adequately treated with:

- A once-a-month paliperidone palmitate extended-release injectable suspension (e.g., INVEGA SUSTENNA) for at least four months or
- An every-three-month paliperidone palmitate extended-release injectable suspension (e.g., INVEGA TRINZA) for at least one three-month cycle. (1)

2 DOSAGE AND ADMINISTRATION

- Administer INVEGA HAFYERA by gluteal injection once every 6 months by a healthcare professional. Do not administer by any other route. (2.1)
- See Full Prescribing Information for complete dosing information. (2.2)
- Initiate INVEGA HAFYERA when the next once-a-month or every three-month paliperidone palmitate extended-release injectable suspension dose is scheduled. Dose is based on the previous once-a-month or every-three-month product. (2.2):
  INVEGA HAFYERA Doses for Adults Adequately Treated with Once-a-month paliperidone palmitate extended-release injectable suspension (PP1M) [Switching from the PP1M 39 mg, 78 mg and 117 mg doses was not studied.]
  If the Last Dose of PP1M is: | Initiate INVEGA HAFYERA at the Following Dose:
  156 mg | 1,092 mg
  234 mg | 1,560 mg
  INVEGA HAFYERA Doses for Adults Adequately Treated with Every-three-month paliperidone palmitate injectable suspension (PP3M) [Switching from the PP3M 273 mg and 410 mg doses was not studied.]
  If the Last Dose of PP3M is: | Initiate INVEGA HAFYERA at the Following Dose:
  546 mg | 1,092 mg
  819 mg | 1,560 mg
- Missed Doses: Refer to the Full Prescribing Information. (2.3)
- See Full Prescribing Information for important preparation and administration information. (2.5)
- Moderate to severe renal impairment (creatinine clearance <50 mL/min): INVEGA HAFYERA is not recommended. (2.4)
- Mild renal impairment (creatinine clearance ≥ 50 mL/min to < 80 mL/min): Adjust dosage and stabilize the patient using PP1M before transitioning to INVEGA HAFYERA, or from PP1M to PP3M before transitioning to INVEGA HAFYERA. See appropriate table above. (2.4)

3 DOSAGE FORMS AND STRENGTHS

Extended-release injectable suspension: 1,092 mg/3.5 mL or 1,560 mg/5 mL single-dose prefilled syringes. (3)

4 CONTRAINDICATIONS

Known hypersensitivity to paliperidone, risperidone, or to any excipients in INVEGA HAFYERA. (4)

5 WARNINGS AND PRECAUTIONS

- Cerebrovascular Adverse Reactions in Elderly Patients with Dementia-Related Psychosis: Increased incidence of cerebrovascular adverse reactions (e.g., stroke, transient ischemic attack, including fatalities). (5.2)
- Neuroleptic Malignant Syndrome: Manage with immediate discontinuation of drug and close monitoring. (5.3)
- QT Prolongation: Avoid use with drugs that also increase QT interval and in patients with risk factors for prolonged QT interval. (5.4)
- Tardive Dyskinesia: Discontinue treatment if clinically appropriate (5.5)
- Metabolic Changes: Monitor for hyperglycemia/diabetes mellitus, dyslipidemia, and weight gain. (5.6)
- Orthostatic Hypotension and Syncope: Use with caution in patients with known cardiovascular or cerebrovascular disease and patients predisposed to hypotension. (5.7)
- Leukopenia, Neutropenia, and Agranulocytosis: Perform complete blood counts (CBC) in patients with pre-existing low white blood cell count (WBC) or a history of leukopenia or neutropenia. Consider discontinuing INVEGA HAFYERA if a clinically significant decline in WBC occurs in the absence of other causative factors. (5.9)
- Hyperprolactinemia: Prolactin elevations occur and persist during chronic administration. (5.10)
- Potential for Cognitive and Motor Impairment: Use caution when operating machinery. (5.11)
- Seizures: Use cautiously in patients with a history of seizures or with conditions that lower the seizure threshold. (5.12)

6 ADVERSE REACTIONS

The most common adverse reactions were upper respiratory tract infection, injection site reaction, weight increased, headache, and parkinsonism. (6.1)

To report SUSPECTED ADVERSE REACTIONS, contact Janssen Pharmaceuticals, Inc. at 1-800-526-7736 or FDA at 1-800-FDA-1088 or www.fda.gov/medwatch.

7 DRUG INTERACTIONS

Strong CYP3A4/P-glycoprotein (P-gp) inducers: Avoid using strong CYP3A4 and/or P-gp inducers during a dosing interval for INVEGA HAFYERA. If administering a strong inducer is necessary, consider managing the patient using paliperidone extended-release tablets. (7.1, 12.3)

8 USE IN SPECIFIC POPULATIONS

- Pregnancy: May cause extrapyramidal and/or withdrawal symptoms in neonates with third trimester exposure. (8.1)

FULL PRESCRIBING INFORMATION

WARNING: INCREASED MORTALITY IN ELDERLY PATIENTS WITH DEMENTIA-RELATED PSYCHOSIS

Elderly patients with dementia-related psychosis treated with antipsychotic drugs are at an increased risk of death. INVEGA HAFYERA is not approved for use in patients with dementia-related psychosis [see Warnings and Precautions (5.1)] .

1 INDICATIONS AND USAGE

INVEGA HAFYERA, an every-six-month injection, is indicated for the treatment of schizophrenia in adults after they have been adequately treated with:

- A once-a-month paliperidone palmitate extended-release injectable suspension (e.g., INVEGA SUSTENNA) for at least four months, or
- An every-three-month paliperidone palmitate extended-release injectable suspension (e.g., INVEGA TRINZA) for at least one three-month cycle.

2 DOSAGE AND ADMINISTRATION

2.1 Important Dosage and Administration Information

- INVEGA HAFYERA must be administered as a gluteal intramuscular injection by a healthcare professional once every 6 months. Do not administer by any other route [see Dosage and Administration (2.5)] .
- Initiate INVEGA HAFYERA only after adequate treatment has been established with either:
  - A once-a-month paliperidone palmitate extended-release injectable suspension (e.g., INVEGA SUSTENNA), referred to as PP1M, once monthly for at least four months; or
  - An every-three-month paliperidone palmitate extended-release injectable suspension (e.g., INVEGA TRINZA), referred to as PP3M, once every three months for at least one three-month injection cycle.
- See Prescribing Information of the PP1M and PP3M products for the recommended dosage of these products.

2.2 Recommended Dosage for INVEGA HAFYERA

Switching to INVEGA HAFYERA from a PP1M Product

The recommended initial INVEGA HAFYERA dose is based on the previous PP1M dose (see Table 1). Initiate INVEGA HAFYERA when the next PP1M dose is scheduled. INVEGA HAFYERA may be administered up to 1 week before or 1 week after the next scheduled PP1M dose. When switching from PP1M to INVEGA HAFYERA, the two injection cycles immediately preceding the switch should be the same dosage strength before starting INVEGA HAFYERA.

Table 1. Initial INVEGA HAFYERA Dose for Adult Patients Switching from a PP1M [PP1M: Once-a-month paliperidone palmitate extended-release injectable suspension] Product
Last Dose of PP1M [There are no equivalent doses of INVEGA HAFYERA for 39 mg, 78 mg, or 117 mg doses of a PP1M product, which were not studied [see Clinical Studies (14)] .] | Initial Dose of INVEGA HAFYERA
156 mg | 1,092 mg
234 mg | 1,560 mg

Switching to INVEGA HAFYERA from a PP3M Product

The recommended initial INVEGA HAFYERA dose is based on the previous PP3M dose (see Table 2). Initiate INVEGA HAFYERA when the next PP3M dose is scheduled. INVEGA HAFYERA may be administered up to 2 weeks before or 2 weeks after the next scheduled PP3M dose.

Table 2. Initial INVEGA HAFYERA Dose for Adult Patients Switching from a PP3M [PP3M: Every-three-month paliperidone palmitate extended-release injectable suspension] Product
Last Dose of PP3M [There are no equivalent doses of INVEGA HAFYERA for the 273 mg or 410 mg doses of a PP3M product, which were not studied [see Clinical Studies (14)] .] | Initial Dose of INVEGA HAFYERA
546 mg | 1,092 mg
819 mg | 1,560 mg

Dosing Interval and Dosage Adjustments of INVEGA HAFYERA

Following the initial dose, administer INVEGA HAFYERA once every 6 months.

If needed, dosage adjustment can be made every 6 months between the dose of 1,092 mg to 1,560 mg based on individual response and tolerability. Because of the potential longer duration of INVEGA HAFYERA, the patient's response to an adjusted dose may not be apparent for several months [see Clinical Pharmacology (12.3)] .

2.3 Missed Doses

Dosing Window

To avoid a missed dose, patients may be given the injection up to 2 weeks before or 3 weeks after the scheduled 6-month dose.

Missed Dose

If a dose of INVEGA HAFYERA is missed, re-initiate with a PP1M product using the re-initiation regimens described in Tables 3 and 4.

More than 6 Months and 3 Weeks, up to but Less than 8 Months Since Last Dose

If more than 6 months and 3 weeks but less than 8 months have elapsed since the last dose of INVEGA HAFYERA, do not administer the next dose of INVEGA HAFYERA. Instead, use the re-initiation regimen shown in Table 3:

Table 3. Re-initiation Regimen for Missed Dose (more than 6 months and 3 weeks, but less than 8 months since last dose)
Last Dose of INVEGA HAFYERA | Administer PP1M Product [PP1M: Once-a-month paliperidone palmitate extended-release injectable suspension] into deltoid muscle | Administer INVEGA HAFYERA into gluteal muscle
 | Day 1 | 1 month after Day 1
1,092 mg | 156 mg | 1,092 mg
1,560 mg | 234 mg | 1,560 mg

8 Months Up to and including 11 Months Since Last Dose

If 8 months but up to and including 11 months have elapsed since the last dose of INVEGA HAFYERA, do not administer the next dose of INVEGA HAFYERA. Instead, use the re-initiation regimen shown in Table 4:

Table 4. Re-initiation Regimen for Missed Dose (8 months up to and including 11 months since last dose)
Last dose of INVEGA HAFYERA | Administer PP1M Product [PP1M: Once-a-month paliperidone palmitate extended-release injectable suspension] into deltoid muscle |  | Administer INVEGA HAFYERA into gluteal muscle
 | Day 1 | Day 8 | 1 month after Day 8
1,092 mg | 156 mg | 156 mg | 1,092 mg
1,560 mg | 156 mg | 156 mg | 1,560 mg

More than 11 Months Since Last Dose

If more than 11 months have elapsed since the last dose of INVEGA HAFYERA, re-initiate treatment with a PP1M product as described in the prescribing information for that product. INVEGA HAFYERA can then be resumed after the patient has been adequately treated with a PP1M product for at least 4 months.

2.4 Dosage Recommendations in Patients with Renal Impairment

INVEGA HAFYERA has not been systematically studied in patients with renal impairment [see Clinical Pharmacology (12.3)] . For patients with mild renal impairment (creatinine clearance ≥50 mL/min to < 80 mL/min [Cockcroft-Gault Formula]), adjust dosage and stabilize the patient using PP1M before transitioning from PP1M to INVEGA HAFYERA, or from PP1M to PP3M before transitioning to INVEGA HAFYERA (see Table 1) [see Use in Specific Populations (8.6)and Clinical Pharmacology (12.3)]. Refer to the Prescribing Information of PP1M or PP3M product for the recommended PP1M or PP3M dosage in patients with mild renal impairment.

INVEGA HAFYERA is not recommended in patients with moderate or severe renal impairment (creatinine clearance <50 mL/min) [see Use in Specific Populations (8.6)and Clinical Pharmacology (12.3)] .

2.5 Instructions for Preparation and Administration

- To be prepared and administered by a healthcare provider only.
- Read the instructions for preparation and administration below and consider referring to the separate Healthcare Provider "Instructions for Use" for preparation and administration considerations.
- For gluteal intramuscular injection only. Do not inject by any other route. As a universal precaution, always wear gloves.
- Inspect INVEGA HAFYERA for particulate matter and discoloration prior to administration.
- Do not mix with any other product or diluent.
- After shaking, INVEGA HAFYERA should appear uniform, thick and milky white .
- Do not use needles from the PP1M or PP3M products or other commercially-available needles to reduce the risk of blockage.
- Avoid inadvertent injection into a blood vessel. Administer the dose in a single injection; do not administer the dose in divided injections. Inject slowly, deep into the upper-outer quadrant of the gluteal muscle. Future injections should be alternated between the two gluteal muscles.

Incomplete Administration

- Proper shaking can reduce the likelihood for an incomplete injection. Storing the carton in a horizontal orientation improves the ability to resuspend this highly concentrated product [see How Supplied/Storage and Handling (16)] .
- Follow the full instructions for preparation and administration to avoid an incomplete injection.
- In the event of an incompletely administered dose, do not re-inject the dose remaining in the syringe and do not administer another dose of INVEGA HAFYERA.
- Closely monitor and treat the patient with oral paliperidone supplementation as clinically appropriate until the next scheduled 6-month injection of INVEGA HAFYERA. See Prescribing Information of the oral paliperidone product for the recommended dosage of these products.

Administer every 6 months

INVEGA HAFYERA (paliperidone palmitate) Shake syringe with the syringe tip cap pointing up VERY FAST for at least 15 seconds, rest briefly, then shake again for 15 seconds.
For Gluteal Intramuscular injection only.

Preparation

INVEGA HAFYERA requires longer and faster shaking than once-a-month paliperidone palmitate extended-release injectable suspension (e.g., INVEGA SUSTENNA).
INVEGA HAFYERA must be administered by a healthcare professional as a single injection. Do not divide dose into multiple injections.
INVEGA HAFYERA is intended for gluteal intramuscular use only. Inject slowly, deep into the muscle taking care to avoid injection into a blood vessel.

Dosing

Administer INVEGA HAFYERA once every 6 months.

Thin Wall Safety Needle

Thin wall safety needle is designed to be used with INVEGA HAFYERA. Therefore, it is important to only use the needle provided in the INVEGA HAFYERA suspension kit.

Dose pack contents Prefilled Syringe

Thin Wall Safety Needle
20G × 1½"
Only use the needle included in this kit

1. Prepare for the injection: this highly concentrated product requires specific steps to resuspend

Hold syringe with the tip cap pointing up

Syringe tip cap pointing up

Shake syringe VERY FAST for at least 15 seconds, rest briefly, then shake again for 15 seconds
To ensure complete resuspension shake syringe with:

- Short, VERY FAST up and down motion
- Loose wrist

Proceed to the next step immediately after shaking.

Check suspension for solid product

Mixed well

Not mixed well
STOP

- Uniform, thick and milky white
- It is normal to see air bubbles

- Solid product on sides and top of syringe
- Uneven mix
- Thin liquid

Product may clog.

Shake syringe with the syringe tip cap pointing up VERY FAST for at least 15 seconds, rest, then shake again for 15 seconds.

Open needle pouch | Peel off the pouch cover. Place pouch with the needle inside on a clean surface.
Remove syringe tip cap and attach needle | Hold the syringe with the tip cap pointing up. Twist and pull off the cap. Attach the safety needle to the syringe using a gentle twisting motion to avoid needle hub cracks or damage. Always check for signs of damage or leakage prior to administration.

Pull back plunger
Hold the syringe upright.
Gently pull back the plunger to clear the syringe tip of any solid product. This will make pressing the plunger easier during the injection.

Remove air bubbles
Press the plunger carefully until a drop of liquid comes out of the needle tip.

2. Slowly inject entire content and confirm

Select and clean a gluteal injection site
Wipe the gluteal site with an alcohol swab and allow it to dry.
Do not touch, fan or blow on the injection site after you have cleaned it.

Remove needle sheath
Pull the needle sheath away from the needle in a straight motion.
Do not twist the sheath, as this may loosen the needle from the syringe.

Slowly inject and confirm
Use slow, firm, consistent pressure to press the plunger completely. This should take approximately 30 seconds.
Continue to press the plunger if you feel resistance. This is normal.

Remove needle from the muscle.

3. After the injection

Secure needle
After the injection is complete, use your thumb or a flat surface to secure the needle in the safety device.
The needle is secure when you hear a "click" sound.

Dispose of properly and check injection site
Dispose of the syringe in an approved sharps container.
There may be a small amount of blood or liquid at the injection site. Hold pressure over the skin with a cotton ball or gauze pad until any bleeding stops.
Do not rub the injection site.
If needed, cover injection site with a bandage.

3 DOSAGE FORMS AND STRENGTHS

INVEGA HAFYERA is a white to off-white aqueous extended-release injectable suspension for gluteal intramuscular injection in dose strengths of 1,092 mg/3.5 mL and 1,560 mg/5 mL paliperidone palmitate in single-dose prefilled syringes.

4 CONTRAINDICATIONS

INVEGA HAFYERA is contraindicated in patients with a known hypersensitivity to either paliperidone or risperidone, or to any of the excipients in the INVEGA HAFYERA formulation. Hypersensitivity reactions, including anaphylactic reactions and angioedema, have been reported in patients treated with risperidone and in patients treated with paliperidone. Paliperidone palmitate is converted to paliperidone, which is a metabolite of risperidone.

5 WARNINGS AND PRECAUTIONS

5.1 Increased Mortality in Elderly Patients with Dementia-Related Psychosis

Elderly patients with dementia-related psychosis treated with antipsychotic drugs are at an increased risk of death. Analyses of 17 placebo-controlled trials (modal duration of 10 weeks), largely in patients taking atypical antipsychotic drugs, revealed a risk of death in drug-treated patients of between 1.6 to 1.7 times the risk of death in placebo-treated patients. Over the course of a typical 10-week controlled trial, the rate of death in drug-treated patients was about 4.5%, compared to a rate of about 2.6% in the placebo group. Although the causes of death were varied, most of the deaths appeared to be either cardiovascular (e.g., heart failure, sudden death) or infectious (e.g., pneumonia) in nature. Observational studies suggest that, similar to atypical antipsychotic drugs, treatment with conventional antipsychotic drugs may increase mortality. The extent to which the findings of increased mortality in observational studies may be attributed to the antipsychotic drug as opposed to some characteristic(s) of the patients is not clear. INVEGA HAFYERA is not approved for the treatment of patients with dementia-related psychosis [see Boxed Warning and Warnings and Precautions (5.2)] .

5.2 Cerebrovascular Adverse Reactions, Including Stroke, in Elderly Patients with Dementia-Related Psychosis

In placebo-controlled trials with risperidone, aripiprazole, and olanzapine in elderly subjects with dementia, there was a higher incidence of cerebrovascular adverse reactions (cerebrovascular accidents and transient ischemic attacks) including fatalities compared to placebo-treated subjects. No studies have been conducted with oral paliperidone, the 1-month paliperidone palmitate extended-release injectable suspension, the 3-month paliperidone extended-release injectable suspension or INVEGA HAFYERA in elderly patients with dementia. These medications are not approved for the treatment of patients with dementia-related psychosis [see Boxed Warning and Warnings and Precautions (5.1)] .

5.3 Neuroleptic Malignant Syndrome

Neuroleptic Malignant Syndrome (NMS), a potentially fatal symptom complex, has been reported in association with antipsychotic drugs, including paliperidone.

Clinical manifestations of NMS are hyperpyrexia, muscle rigidity, altered mental status, including delirium, and autonomic instability (irregular pulse or blood pressure, tachycardia, diaphoresis, and cardiac dysrhythmia). Additional signs may include elevated creatine phosphokinase, myoglobinuria (rhabdomyolysis), and acute renal failure.

If NMS is suspected, discontinue INVEGA HAFYERA and provide symptomatic treatment and monitoring.

5.4 QT Prolongation

Paliperidone causes a modest increase in the corrected QT (QTc) interval. The use of paliperidone should be avoided in combination with other drugs that are known to prolong QTc including Class 1A (e.g., quinidine, procainamide) or Class III (e.g., amiodarone, sotalol) antiarrhythmic medications, antipsychotic medications (e.g., chlorpromazine, thioridazine), antibiotics (e.g., gatifloxacin, moxifloxacin), or any other class of medications known to prolong the QTc interval. Paliperidone should also be avoided in patients with congenital long QT syndrome and in patients with a history of cardiac arrhythmias.

Certain circumstances may increase the risk of the occurrence of Torsades de pointes and/or sudden death in association with the use of drugs that prolong the QTc interval, including (1) bradycardia; (2) hypokalemia or hypomagnesemia; (3) concomitant use of other drugs that prolong the QTc interval; and (4) presence of congenital prolongation of the QT interval.

The effects of paliperidone on the QT interval were evaluated in a double-blind, active-controlled (moxifloxacin 400 mg single dose), multicenter Thorough QT study with oral paliperidone in adult patients, and in four fixed-dose efficacy studies and one maintenance study of the 1-month paliperidone palmitate injectable product.

In the Thorough QT study (n=141), the 8 mg dose of immediate-release oral paliperidone (n=50) showed a mean placebo-subtracted increase from baseline in QTcLD (QT interval corrected for heart rate using the population specified linear derived method) of 12.3 msec (90% CI: 8.9; 15.6) on day 8 at 1.5 hours post-dose. The mean steady-state peak plasma concentration for this 8 mg dose of paliperidone immediate release (Cmax ss=113 ng/mL) was approximately 1.3-fold the exposure with the maximum recommended 1,560 mg dose of INVEGA HAFYERA administered in the gluteal muscle (mean Cmax md=89.3 ng/mL). In this same study, a 4 mg dose of the immediate-release oral formulation of paliperidone, for which Cmax ss=35 ng/mL, showed an increased placebo-subtracted QTcLD of 6.8 msec (90% CI: 3.6; 10.1) on day 2 at 1.5 hours post-dose.

In the four fixed-dose efficacy studies of the 1-month paliperidone palmitate injectable product, no subject had a change in QTcLD exceeding 60 msec and no subject had a QTcLD value of >500 msec at any time point. In the maintenance study, no subject had a QTcLD change >60 msec, and one subject had a QTcLD value of 507 msec (Bazett's QT corrected interval [QTcB] value of 483 msec); this latter subject also had a heart rate of 45 beats per minute.

In the INVEGA HAFYERA randomized double-blind active controlled study in subjects with schizophrenia, during the double-blind Phase, QTcLD exceeding 60 msec was observed in 2 subjects (0.4%) in the INVEGA HAFYERA treatment group and in 2 subjects (0.9%) in the PP3M treatment group. No subject had a QTcLD value of >480 msec at any point in the study.

5.5 Tardive Dyskinesia

Tardive dyskinesia, a syndrome of potentially irreversible, involuntary, dyskinetic movements, may develop in patients treated with antipsychotic drugs. Although the prevalence of the syndrome appears to be highest among the elderly, especially elderly women, it is impossible to predict which patients will develop the syndrome. Whether antipsychotic drug products differ in their potential to cause tardive dyskinesia is unknown.

The risk of developing tardive dyskinesia and the likelihood that it will become irreversible appear to increase as the duration of treatment and the total cumulative dose. The syndrome can develop after relatively brief treatment periods, even at low doses. It may also occur after discontinuation of treatment.

Tardive dyskinesia may remit, partially or completely, if antipsychotic treatment is discontinued. Antipsychotic treatment itself may suppress (or partially suppress) the signs and symptoms of the syndrome and may thus mask the underlying process. The effect of symptomatic suppression on the long-term course of the syndrome is unknown.

Given these considerations, INVEGA HAFYERA should be prescribed in a manner that is most likely to minimize the occurrence of tardive dyskinesia. Chronic antipsychotic treatment should generally be reserved for patients who suffer from a chronic illness that is known to respond to antipsychotic drugs. In patients who do require chronic treatment, the smallest dose and the shortest duration of treatment producing a satisfactory clinical response should be sought. The need for continued treatment should be reassessed periodically.

If signs and symptoms of tardive dyskinesia appear in a patient treated with INVEGA HAFYERA, drug discontinuation should be considered. Consideration should be given to the long-acting nature of INVEGA HAFYERA. However, some patients may require treatment with INVEGA HAFYERA despite the presence of the syndrome.

5.6 Metabolic Changes

Atypical antipsychotic drugs have been associated with metabolic changes that may increase cardiovascular/cerebrovascular risk. These metabolic changes include hyperglycemia, dyslipidemia, and body weight gain. While all of the drugs in the class have been shown to produce some metabolic changes, each drug has its own specific risk profile.

Hyperglycemia and Diabetes Mellitus

Hyperglycemia and diabetes mellitus, in some cases extreme and associated with ketoacidosis or hyperosmolar coma or death, have been reported in patients treated with all atypical antipsychotics. These cases were, for the most part, seen in post-marketing clinical use and epidemiologic studies, not in clinical trials. Hyperglycemia and diabetes have been reported in trial subjects treated with INVEGA HAFYERA. Assessment of the relationship between atypical antipsychotic use and glucose abnormalities is complicated by the possibility of an increased background risk of diabetes mellitus in patients with schizophrenia and the increasing incidence of diabetes mellitus in the general population. Given these confounders, the relationship between atypical antipsychotic use and hyperglycemia-related adverse events is not completely understood. However, epidemiological studies suggest an increased risk of hyperglycemia-related adverse reactions in patients treated with the atypical antipsychotics.

Patients with an established diagnosis of diabetes mellitus who are started on atypical antipsychotics should be monitored regularly for worsening of glucose control. Patients with risk factors for diabetes mellitus (e.g., obesity, family history of diabetes) who are starting treatment with atypical antipsychotics should undergo fasting blood glucose testing at the beginning of treatment and periodically during treatment. Any patient treated with atypical antipsychotics should be monitored for symptoms of hyperglycemia including polydipsia, polyuria, polyphagia, and weakness. Patients who develop symptoms of hyperglycemia during treatment with atypical antipsychotics should undergo fasting blood glucose testing. In some cases, hyperglycemia has resolved when the atypical antipsychotic was discontinued; however, some patients required continuation of anti-diabetic treatment despite discontinuation of the suspect drug.

Data from the randomized double-blind active controlled study with INVEGA HAFYERA in patients with schizophrenia are presented in Table 5.

Table 5. Change in Fasting Glucose from the randomized double-blind active controlled study with INVEGA HAFYERA in patients with schizophrenia
Total no. of patients [The number of subjects with paired fasting data (baseline and any post baseline assessment). Using the conversion factor (1 mg/dL=0.05551 mmol/L) the ADA specified limits are as follows: Normal: <100 mg/dL (<5.551 mmol/L) Impaired: ≥100 mg/dL (≥5.551 mmol/L) to <126 mg/dL (<6.994 mmol/L) High: ≥126 mg/dL (≥6.994 mmol/L) 126 mg/dL=6.994 mmol/L; 140 mg/dL=7.771 mmol/L; 200 mg/dL=11.102 mmol/L; 300 mg/dL=16.653 mmol/L] | PP3M [PP3M – Every-three-month paliperidone palmitate extended-release injectable suspension] N=195 | INVEGA HAFYERA N=423
Normal to high | 3% | 4%
Impaired glucose tolerance to high | 4% | 5%
Normal/impaired glucose tolerance to high | 7% | 9%
<126 mg/dL to >=140 mg/dL | 4% | 5%
<126 mg/dL to >=200 mg/dL | 0 | 1%
<126 mg/dL to >=300 mg/dL | 0 | <1%

Dyslipidemia

Undesirable alterations in lipids have been observed in patients treated with atypical antipsychotics.

Shifts in lipid parameters from the randomized double-blind active controlled study with INVEGA HAFYERA in patients with schizophrenia are presented in Table 6.

Table 6. Shifts in Fasting Lipids in the Double-Blind Phase from the randomized active controlled study with INVEGA HAFYERA in patients with schizophrenia
 | PP3M [PP3M – Every-three-month paliperidone palmitate extended-release injectable suspension.] N=194 | INVEGA HAFYERA N=423
Fasting Cholesterol (mg/dL)
<200 mg/dL to >=240 mg/dL | 2 (1%) | 3 (0.7%)
Fasting HDL Cholesterol (mg/dL)
>=40 mg/dL to <40 mg/dL | 28 (14%) | 55 (13%)
Fasting LDL Cholesterol (mg/dL)
<100 mg/dL to >=160 mg/dL | 1 (0.5%) | 2 (0.5%)
Fasting Triglycerides (mg/dL)
<150 mg/dL to >=200 mg/dL | 22 (11%) | 22 (5%)
For each fasting parameter, subjects with both Baseline (DB) record and any post baseline (DB) record during Double-Blind Phase are included in the denominator.

Change in Body Weight

Weight gain has been observed with atypical antipsychotic use. Clinical monitoring of weight is recommended. In the randomized active controlled clinical study of INVEGA HAFYERA, the overall mean weight change during the double-blind Phase was similar to PP3M.

5.7 Orthostatic Hypotension and Syncope

Paliperidone can induce orthostatic hypotension and syncope in some patients because of its alpha-adrenergic blocking activity.

Use INVEGA HAFYERA with caution in patients with known cardiovascular disease (e.g., heart failure, history of myocardial infarction or ischemia, conduction abnormalities), cerebrovascular disease, or conditions that predispose the patient to hypotension (e.g., dehydration, hypovolemia, and treatment with antihypertensive medications). Monitoring of orthostatic vital signs should be considered in patients who are vulnerable to hypotension.

5.8 Falls

Somnolence, postural hypotension, motor and sensory instability have been reported with the use of antipsychotics, including paliperidone palmitate, which may lead to falls and, consequently, fractures or other fall-related injuries. For patients, particularly the elderly, with diseases, conditions, or medications that could exacerbate these effects, assess the risk of falls when initiating antipsychotic treatment and recurrently for patients on long-term antipsychotic therapy.

5.9 Leukopenia, Neutropenia, and Agranulocytosis

In clinical trial and/or postmarketing experience, events of leukopenia and neutropenia have been reported temporally related to antipsychotic agents, including INVEGA HAFYERA. Agranulocytosis has also been reported.

Possible risk factors for leukopenia/neutropenia include pre-existing low white blood cell count (WBC)/absolute neutrophil count (ANC) and history of drug-induced leukopenia/neutropenia. In patients with a history of a clinically significant low WBC/ANC or a drug-induced leukopenia/neutropenia, perform a complete blood count (CBC) frequently during the first few months of therapy. In such patients, consider discontinuation of INVEGA HAFYERA at the first sign of a clinically significant decline in WBC in the absence of other causative factors.

Monitor patients with clinically significant neutropenia for fever or other symptoms or signs of infection and treated promptly if such symptoms or signs occur. Discontinue INVEGA HAFYERA in patients with severe neutropenia (absolute neutrophil count <1000/mm^3) and follow their WBC until recovery.

5.10 Hyperprolactinemia

Like other drugs that antagonize dopamine D2receptors, paliperidone elevates prolactin levels and the elevation persists during chronic administration. Paliperidone has a prolactin-elevating effect similar to that seen with risperidone, a drug that is associated with higher levels of prolactin than other antipsychotic drugs.

Hyperprolactinemia, regardless of etiology, may suppress hypothalamic GnRH, resulting in reduced pituitary gonadotrophin secretion. This, in turn, may inhibit reproductive function by impairing gonadal steroidogenesis in both female and male patients. Galactorrhea, amenorrhea, gynecomastia, and impotence have been reported in patients receiving prolactin-elevating compounds. Long-standing hyperprolactinemia when associated with hypogonadism may lead to decreased bone density in both female and male subjects.

Tissue culture experiments indicate that approximately one-third of human breast cancers are prolactin dependent in vitro, a factor of potential importance if the prescription of these drugs is considered in a patient with previously detected breast cancer. An increase in the incidence of pituitary gland, mammary gland, and pancreatic islet cell neoplasia (mammary adenocarcinomas, pituitary and pancreatic adenomas) was observed in the risperidone carcinogenicity studies conducted in mice and rats [see Nonclinical Toxicology (13.1)] . Published epidemiologic studies have shown inconsistent results when exploring the potential association between hyperprolactinemia and breast cancer.

Median prolactin levels remained relatively stable throughout the open-label and double-blind phases in male subjects, whereas in female subjects, median prolactin levels increased. During the double-blind phase, median prolactin levels continued to increase after dosing in both the INVEGA HAFYERA and PP3M groups, returning to baseline level at Month 6 and at Month 12 (end of double-blind phase).

During the double-blind phase, prolactin levels relative to reference range (>13.13 ng/mL in males and >26.72 ng/mL in females) from maintenance baseline were noted in a similar percentage of subjects in the INVEGA HAFYERA and PP3M groups in both males (35% vs 36%) and females (29% vs. 30%). In the INVEGA HAFYERA group, 14 females (2.9%) and 4 males (0.8%) experienced potentially prolactin-related adverse reactions, while 6 females (2.7%) and 1 male (0.4%) in the PP3M experienced potentially prolactin-related adverse reactions.

5.11 Potential for Cognitive and Motor Impairment

Somnolence and sedation were reported as adverse reactions in patients treated with INVEGA HAFYERA [see Adverse Reactions (6.1)] . Antipsychotics, including INVEGA HAFYERA, have the potential to impair judgment, thinking, or motor skills. Patients should be cautioned about performing activities requiring mental alertness, such as operating hazardous machinery or operating a motor vehicle, until they are reasonably certain that paliperidone therapy does not adversely affect them.

5.12 Seizures

In the 6-month paliperidone palmitate extended-release injectable suspension double-blind active controlled trial there were no reports of seizures or convulsions, nor were any reports made in the long-term maintenance trial of PP3M. In the pivotal clinical studies with PP1M which included four fixed-dose, double-blind, placebo-controlled studies in subjects with schizophrenia, <1% (1/1293) of subjects treated with the PP1M experienced an adverse event of convulsion compared with <1% (1/510) of placebo-treated subjects who experienced an adverse event of grand mal convulsion.

Like other antipsychotic drugs, INVEGA HAFYERA should be used cautiously in patients with a history of seizures or other conditions that potentially lower the seizure threshold. Conditions that lower the seizure threshold may be more prevalent in patients 65 years or older.

5.13 Dysphagia

Esophageal dysmotility and aspiration have been associated with antipsychotic drug use. INVEGA HAFYERA and other antipsychotic drugs should be used cautiously in patients at risk for aspiration pneumonia.

5.14 Priapism

A case (0.2%) of priapism was reported in the clinical trial with INVEGA HAFYERA. Priapism has been reported with oral paliperidone during postmarketing surveillance. Drugs with alpha-adrenergic blocking effects have been reported to induce priapism. Severe priapism may require surgical intervention.

5.15 Disruption of Body Temperature Regulation

Disruption of the body's ability to reduce core body temperature has been attributed to antipsychotic agents. Appropriate care is advised when prescribing INVEGA HAFYERA to patients who will be experiencing conditions which may contribute to an elevation in core body temperature, e.g., exercising strenuously, exposure to extreme heat, receiving concomitant medication with anticholinergic activity, or being subject to dehydration.

6 ADVERSE REACTIONS

The following are discussed in more detail in other sections of the labeling:

- Increased mortality in elderly patients with dementia-related psychosis [see Boxed Warning and Warnings and Precautions (5.1)]
- Cerebrovascular adverse reactions, including stroke, in elderly patients with dementia-related psychosis [see Warnings and Precautions (5.2)]
- Neuroleptic malignant syndrome [see Warnings and Precautions (5.3)]
- QT prolongation [see Warnings and Precautions (5.4)]
- Tardive dyskinesia [see Warnings and Precautions (5.5)]
- Metabolic changes [see Warnings and Precautions (5.6)]
- Orthostatic hypotension and syncope [see Warnings and Precautions (5.7)]
- Falls [see Warnings and Precautions (5.8)]
- Leukopenia, neutropenia, and agranulocytosis [see Warnings and Precautions (5.9)]
- Hyperprolactinemia [see Warnings and Precautions (5.10)]
- Potential for cognitive and motor impairment [see Warnings and Precautions (5.11)]
- Seizures [see Warnings and Precautions (5.12)]
- Dysphagia [see Warnings and Precautions (5.13)]
- Priapism [see Warnings and Precautions (5.14)]
- Disruption of body temperature regulation [see Warnings and Precautions (5.15)]

6.1 Clinical Trials Experience

Because clinical trials are conducted under widely varying conditions, adverse reaction rates observed in the clinical trials of a drug cannot be directly compared to rates in the clinical trials of another drug and may not reflect the rates observed in clinical practice.

Patient Exposure

The data described in this section is derived from the randomized double-blind active controlled non-inferiority study of INVEGA HAFYERA and 3-month paliperidone palmitate extended-release injectable suspension. During the double-blind phase, 478 patients were randomized to receive 2 injection cycles of INVEGA HAFYERA over a 12-month duration. The mean (SD) duration of exposure was 329.8 (86.97) days in the INVEGA HAFYERA group and 336.4 (80.89) days in the PP3M group during the double-blind phase:

Adverse Reactions in the Double-Blind, Active-Controlled Clinical Trial

Commonly Observed Adverse Reactions: The most common adverse reactions (incidence at least 5% in the double-blind Phase) of the INVEGA HAFYERA clinical trial were, upper respiratory tract infection, injection site reaction, weight increased, headache and parkinsonism.

Discontinuation of Treatment Due to Adverse Reactions: In the double-blind phase of the INVEGA HAFYERA clinical trial 1.3% of subjects in the INVEGA HAFYERA group and 0.4% of subjects in the 3-month paliperidone palmitate extended-release injectable suspension group discontinued due to adverse reactions.

Adverse Reactions Occurring at an Incidence of 2% or More in INVEGA HAFYERA-Treated Patients: Table 7 lists the adverse reactions reported in the INVEGA HAFYERA clinical trial.

Table 7. Incidences of Adverse Reactions 2% or More of INVEGA HAFYERA-Treated Patients for the Double-Blind Phase of the Randomized Double-blind Active Controlled Trial in Patients with Schizophrenia
 | Double Blind
System Organ Class | PP3M [PP3M – Every-three-month paliperidone palmitate extended-release injectable suspension] (N=224) % | INVEGA HAFYERA (N=478) %
Adverse Reaction
Gastrointestinal disorders
Diarrhea [The following terms were combined: Diarrhea includes: Diarrhea, Diarrhea infectious. Injection site reaction: includes Injection site reaction, Injection site discomfort, Injection site erythema, Injection site hemorrhage, Injection site induration, Injection site nodule, Injection site oedema, Injection site pain, Injection site swelling. Weight increased includes: Weight increased, Body mass index increased, Obesity, Waist circumference increased. Upper respiratory tract infection includes: Upper respiratory tract infection, Nasopharyngitis, Pharyngitis, Rhinitis, Viral pharyngitis, Viral upper respiratory tract infection. Back pain includes: Back pain, Neck pain, Spinal pain. Musculoskeletal pain includes: Musculoskeletal pain, Musculoskeletal chest pain, Myalgia, Pain in extremity. Akathisia includes: Akathisia, Restless legs syndrome, Restlessness. Extrapyramidal symptoms includes: blepharospasms, bradykinesia, drooling, dyskinesia, dystonia, hypokinesia, musculoskeletal stiffness, muscle rigidity, muscle spasms, oculogyric crisis, Parkinsonism, Parkinsonism rest tremor, reduced facial expression, tardive dyskinesia. Insomnia includes: Insomnia, Initial insomnia, Middle insomnia. Psychosis includes: acute psychosis, delusion, delusion of reference, hallucination (auditory), psychotic disorder, psychotic symptom, and schizophrenia.] | 1 | 2
General disorders and administration site conditions
Injection site reaction | 5 | 11
Infections and infestations
Upper respiratory tract infection | 13 | 12
Urinary tract infection | 1 | 3
Metabolism and nutrition disorders
Weight increased | 8 | 9
Musculoskeletal and connective tissue disorders
Back pain | 1 | 3
Musculoskeletal pain | 1 | 3
Nervous system disorders
Akathisia | 4 | 4
Headache | 5 | 7
Extrapyramidal symptoms | 5 | 7
Psychiatric disorders
Psychosis | 3 | 3
Anxiety | 0 | 3
Insomnia | 2 | 3

Demographic Differences

An examination of population subgroups in the INVEGA HAFYERA trial did not reveal any evidence of differences in safety on the basis of age, gender, or race alone.

Extrapyramidal Symptoms (EPS)

Data from the randomized double-blind active controlled study provided information regarding EPS. Several methods were used to measure EPS: (1) the Simpson-Angus Rating Scale Global Score which broadly evaluates parkinsonism, (2) the Barnes Akathisia Rating Scale Global Clinical Rating Score which evaluates akathisia, (3) the Abnormal Involuntary Movement Scale scores which evaluates dyskinesia, and (4) use of anticholinergic medications to treat EPS (Table 8) and (5) incidence of spontaneous reports of EPS (Table 9).

Table 8. Extrapyramidal Symptoms (EPS) Assessed by Rating Scales Incidence and Use of Anticholinergic Medication During the Double-blind Phase
 | PP3M [PP3M - Every-three-month paliperidone palmitate extended-release injectable suspension] (N=224) % | INVEGA HAFYERA (N=478) %
Use of Anticholinergic Medication [Use of Anti-EPS Medication During the Double-blind Phase] | 13 | 15
Parkinsonism [Percent of subjects with Simpson-Angus Scale Global Score >0.3(Global Score defined as total sum of items score divided by the number of items).] | 6 | 7
Akathisia [Percent of subjects with Barnes Akathisia Rating Scale Global Clinical Rating Score ≥2] | 3 | 3
Dyskinesia [Percent of subjects with a score ≥3 on any of the first seven items or a score ≥2 on two or more of any of the first seven items of the Abnormal Involuntary Movement Scale] | 1 | 1
Note: Percentages are calculated based on number of subjects in the DB Safety analysis set per treatment group.

Table 9. Extrapyramidal Symptoms (EPS)-Related Events by MedDRA Preferred Term
 | Double-blind Phase
EPS Group | PP3M [PP3M – Every-three-month paliperidone palmitate extended-release injectable suspension Parkinsonism group includes: Bradykinesia, drooling, hypokinesia, muscle rigidity, musculoskeletal stiffness, parkinsonism, parkinsonian rest tremor, reduced facial expression Hyperkinesia group includes: Akathisia, restlessness, restless legs syndrome Dyskinesia group includes: Dyskinesia, muscle twitching, tardive dyskinesia Dystonia group includes: Blepharospasm, dystonia, muscle spasms, oculogyric crisis] (N=224) % | INVEGA HAFYERA (N=478) %
Overall percentage of subjects with EPS-related adverse events | 9 | 10
Parkinsonism | 4 | 5
Hyperkinesia | 4 | 4
Tremor | 0 | <1
Dyskinesia | 1 | 2
Dystonia | 1 | 1

Dystonia

Symptoms of dystonia, prolonged abnormal contractions of muscle groups, may occur in susceptible individuals during the first few days of treatment. Dystonic symptoms include: spasm of the neck muscles, sometimes progressing to tightness of the throat, swallowing difficulty, difficulty breathing, and/or protrusion of the tongue. While these symptoms can occur at low doses, they occur more frequently and with greater severity with high potency and at higher doses of first-generation antipsychotic drugs. An elevated risk of acute dystonia is observed in males and younger age groups.

Pain Assessment and Local Injection Site Reactions

Investigator ratings of injection site. Induration, redness and swelling were observed in 13% in the INVEGA HAFYERA group and 9% in the PP3M group during the double-blind Phase. Investigator evaluation of tenderness was higher for subjects in the INVEGA HAFYERA group versus the 3-month paliperidone palmitate extended-release injectable suspension group (31% vs. 19%) during the double-blind Phase. Active INVEGA HAFYERA medication was given at double-blind baseline and Month 6, while placebo medication was given at the other injection times.

Subject ratings of injection site pain. The average score for the subject's evaluation of injection pain on a scale of 0 to 100 was approximately 16 at the open-label Phase end point and approximately 5 in both groups at the double-blind Phase end point.

Other Adverse Reactions Observed During the Clinical Trial Evaluation of INVEGA HAFYERA

The following additional adverse reactions were identified in the randomized double-blind active controlled study. The following list does not include reactions: 1) already listed in previous tables or elsewhere in labeling, 2) for which a drug cause was remote, 3) which were so general as to be uninformative, 4) which were not considered to have significant clinical implications.

Blood and lymphatic system disorders: anemia

Cardiac disorders: bradycardia, tachycardia

Ear and labyrinth disorders: vertigo

Gastrointestinal disorders: constipation, nausea, vomiting

General disorders and administration site conditions: fatigue

Hepatobiliary disorders: transaminases increased

Infections and infestations: cystitis, respiratory tract infection, tonsillitis

Metabolism and nutritional disorders: decreased appetite, increased appetite, weight decreased

Psychiatric disorders: depression

Reproductive system and breast disorders: breast pain, menstrual disorder

Skin and subcutaneous tissue disorders: rash

Vascular disorders: hypertension

Additional Adverse Reactions Reported in Clinical Trials with the 1-Month and 3-Month Paliperidone Palmitate Extended-Release Injectable Suspension

The following is a list of additional adverse reactions that have been reported in clinical trials with the 1-month and 3-month paliperidone palmitate extended-release injectable suspensions that are not listed elsewhere:

Cardiac disorders: atrioventricular block first degree, bundle branch block, palpitations, postural orthostatic tachycardia syndrome

Eye disorders: eye movement disorder, eye rolling, oculogyric crisis, vision blurred

Gastrointestinal disorders: abdominal discomfort/abdominal pain upper, diarrhea, dry mouth, toothache

General disorders and administration site conditions: asthenia, chest discomfort

Immune system disorders: hypersensitivity

Investigations: electrocardiogram abnormal

Metabolism and nutrition disorders: hyperinsulinemia

Musculoskeletal and connective tissue disorders: myalgia, pain in extremity, joint stiffness, muscle spasms, muscle twitching, nuchal rigidity

Nervous system disorders: bradykinesia, cerebrovascular accident, convulsion, dizziness, dizziness postural, dysarthria, hypertonia, lethargy, oromandibular dystonia, psychomotor hyperactivity, syncope

Psychiatric disorders: agitation, nightmare

Reproductive system and breast disorders: breast discharge, erectile dysfunction, gynecomastia, sexual dysfunction

Respiratory, thoracic and mediastinal disorders: cough

Skin and subcutaneous tissue disorders: drug eruption, eczema, pruritus, pruritus generalized, urticaria

Vascular disorders: hypotension, orthostatic hypotension

Additional Adverse Reactions Reported in Clinical Trials with Oral Paliperidone

The following is a list of additional adverse reactions that have been reported in clinical trials with oral paliperidone:

Cardiac disorders: bundle branch block left, sinus arrhythmia

Gastrointestinal disorders: abdominal pain, constipation, flatulence, small intestinal obstruction

General disorders and administration site conditions: edema, edema peripheral

Immune system disorders: anaphylactic reaction

Musculoskeletal and connective tissue disorders: arthralgia, torticollis, trismus

Nervous system disorders: grand mal convulsion, parkinsonian gait, transient ischemic attack

Psychiatric disorders: sleep disorder

Reproductive system and breast disorders: breast engorgement, breast tenderness, retrograde ejaculation

Respiratory, thoracic and mediastinal disorders: nasal congestion, pharyngolaryngeal pain, pneumonia aspiration

Skin and subcutaneous tissue disorders: rash papular

Vascular disorders: ischemia

6.2 Postmarketing Experience

The following adverse reactions have been identified during post-approval use of paliperidone; because these reactions were reported voluntarily from a population of uncertain size, it is not always possible to reliably estimate their frequency or establish a causal relationship to drug exposure: angioedema, catatonia, ileus, somnambulism, swollen tongue, thrombotic thrombocytopenic purpura, urinary incontinence, and urinary retention.

Cases of anaphylactic reaction after injection with the 1-month paliperidone palmitate extended-release suspension have been reported during postmarketing experience in patients who have previously tolerated oral risperidone or oral paliperidone.

Paliperidone is the major active metabolite of risperidone. Adverse reactions reported with oral risperidone and risperidone long-acting injection can be found in the Adverse Reactions (6)section of the Prescribing Information for those products.

7 DRUG INTERACTIONS

7.1 Drugs Having Clinically Important Interactions with INVEGA HAFYERA

Because paliperidone palmitate is hydrolyzed to paliperidone, results from studies with oral paliperidone should be taken into consideration when assessing drug-drug interaction potential. In addition, consider the 6-month dosing interval and the half-life of INVEGA HAFYERA [see Clinical Pharmacology (12.3)] .

Table 10 presents clinically significant drug interactions with INVEGA HAFYERA.

Table 10. Clinically Important Drug Interactions with INVEGA HAFYERA
Centrally acting Drugs and Alcohol
Clinical Rationale | Given the primary CNS effects of paliperidone, concomitant use of centrally acting drugs and alcohol may modulate the CNS effects of INVEGA HAFYERA.
Clinical Recommendation | INVEGA HAFYERA should be used with caution with other centrally acting drugs and alcohol.
Drugs with Potential for Inducing Orthostatic Hypotension
Clinical Rationale | Because INVEGA HAFYERA has the potential for inducing orthostatic hypotension, an additive effect may occur when INVEGA HAFYERA is administered with other therapeutic agents that have this potential [see Warnings and Precautions (5.7)] .
Clinical Recommendation | Monitor orthostatic vital signs in patients who are vulnerable to hypotension [see Warnings and Precautions (5.7)] .
Strong Inducers of CYP3A4 and P-gp
Clinical Rationale | The concomitant use of INVEGA HAFYERA and strong inducers of CYP3A4 and P-gp may decrease the exposure of paliperidone [see Clinical Pharmacology (12.3)] .
Clinical Recommendation | Avoid using CYP3A4 and/or P-gp inducers with INVEGA HAFYERA during the 6-month dosing interval, if possible. If administering a strong inducer is necessary, consider managing the patient using paliperidone extended-release tablets [see Dosage and Administration (2.1)] .
Examples | carbamazepine, rifampin, or St. John's Wort
Levodopa and Other Dopamine Agonists
Clinical Rationale | Paliperidone may antagonize the effect of levodopa and other dopamine agonists.
Clinical Recommendation | Monitor and manage patient as clinically appropriate.

7.2 Drugs Having No Clinically Important Interactions with INVEGA HAFYERA

Based on pharmacokinetic studies with oral paliperidone, no dosage adjustment of INVEGA HAFYERA is required when administered concomitantly with valproate [see Clinical Pharmacology (12.3)] . Additionally, no dosage adjustment is necessary for valproate when co-administered with INVEGA HAFYERA [see Clinical Pharmacology (12.3)] .

Pharmacokinetic interaction between lithium and INVEGA HAFYERA is unlikely.

Paliperidone is not expected to cause clinically important pharmacokinetic interactions with drugs that are metabolized by cytochrome P450 isozymes. In vitro studies indicate that CYP2D6 and CYP3A4 may be involved in paliperidone metabolism; however, there is no evidence in vivo that inhibitors of these enzymes significantly affect the metabolism of paliperidone. Paliperidone is not a substrate of CYP1A2, CYP2A6, CYP2C9, and CYP2C19; an interaction with inhibitors or inducers of these isozymes is unlikely [see Clinical Pharmacology (12.3)].

8 USE IN SPECIFIC POPULATIONS

8.1 Pregnancy

Pregnancy Exposure Registry

There is a pregnancy exposure registry that monitors pregnancy outcomes in women exposed to atypical antipsychotics, including INVEGA HAFYERA, during pregnancy. Healthcare providers are encouraged to register patients by contacting the National Pregnancy Registry for Atypical Antipsychotics at 1-866-961-2388 or online at http://womensmentalhealth.org/clinical-and-research-programs/pregnancyregistry/.

Risk Summary

Neonates exposed to antipsychotic drugs during the third trimester of pregnancy are at risk for extrapyramidal and/or withdrawal symptoms following delivery (see Clinical Considerations) . Overall, available data from published epidemiologic studies of pregnant women exposed to paliperidone have not established a drug-associated risk for major birth defects, miscarriage, or adverse maternal or fetal outcomes (see Data) . There are risks to the mother associated with untreated schizophrenia and with exposure to antipsychotics, including INVEGA HAFYERA during pregnancy (see Clinical Considerations) . Paliperidone has been detected in plasma in adult subjects up to 18 months after a single-dose administration of 3-month paliperidone palmitate extended-release injectable suspension. [See Clinical Pharmacology (12.3)] . The clinical significance of INVEGA HAFYERA administered before pregnancy or anytime during pregnancy is not known.

The estimated background risk of major birth defects and miscarriage for the indicated population is unknown. All pregnancies have a background risk of birth defects, loss, or other adverse outcomes. In the U.S. general population, the estimated background risk of major birth defects and miscarriage in clinically recognized pregnancies is 2 to 4% and 15 to 20%, respectively.

In animal reproduction studies, there were no treatment related effects on the offspring when pregnant rats were injected intramuscularly with paliperidone palmitate or when pregnant rats and rabbits were treated orally with paliperidone during the period of organogenesis. Additional reproduction toxicity studies were conducted with orally administered risperidone, which is extensively converted to paliperidone (see Animal Data) .

Clinical Considerations

Disease-associated maternal and/or embryo/fetal risk

There is a risk to the mother from untreated schizophrenia, including increased risk of relapse, hospitalization, and suicide. Schizophrenia is associated with increased adverse perinatal outcomes, including preterm birth. It is not known if this is a direct result of the illness or other comorbid factors.

Fetal/Neonatal Adverse Reactions

Extrapyramidal and/or withdrawal symptoms, including agitation, hypertonia, hypotonia, tremor, somnolence, respiratory distress, and feeding disorder have been reported in neonates who were exposed to antipsychotic drugs, including INVEGA HAFYERA, during the third trimester of pregnancy. These symptoms have varied in severity. Monitor neonates for extrapyramidal and/or withdrawal symptoms and manage symptoms appropriately. Some neonates recovered within hours or days without specific treatment; others required prolonged hospitalization.

Data

Human Data

Published data from observational studies, birth registries, and case reports on the use of atypical antipsychotics during pregnancy do not report a clear association with antipsychotics and major birth defects. A prospective observational study including 6 women treated with risperidone, the parent compound of paliperidone, demonstrated placental passage of risperidone and paliperidone. A retrospective cohort study from a Medicaid database of 9258 women exposed to antipsychotics during pregnancy did not indicate an overall increased risk for major birth defects. There was a small increase in the risk of major birth defects (RR=1.26, 95% CI 1.02–1.56) and of cardiac malformations (RR=1.26, 95% CI 0.88–1.81) in a subgroup of 1566 women exposed to the parent compound of paliperidone, risperidone, during the first trimester of pregnancy; however, there is no mechanism of action to explain the difference in malformation rates.

Animal Data

No developmental toxicity studies were conducted with the 6-month paliperidone palmitate extended-release injectable suspension.

There were no treatment-related effects on the offspring when pregnant rats were injected intramuscularly with 1-month paliperidone palmitate extended-release injectable suspension during the period of organogenesis at doses up to 250 mg/kg, which is ~10 times the MRHD of 234 mg of the 1-month paliperidone palmitate extended-release injectable suspension based on mg/m^2 body surface area.

In animal reproduction studies, there were no increases in fetal abnormalities when pregnant rats and rabbits were treated orally with paliperidone during the period of organogenesis with up to 8 times the oral MRHD of 12 mg based on mg/m^2 body surface area.

Additional reproduction toxicity studies were conducted with orally administered risperidone, which is extensively converted to paliperidone. Cleft palate was observed in the offspring of pregnant mice treated with risperidone at 3 to 4 times the MRHD of 16 mg based on mg/m^2 body surface area; maternal toxicity occurred at 4 times the MRHD. There was no evidence of teratogenicity in embryo-fetal developmental toxicity studies with risperidone in rats and rabbits at doses up to 6 times the MRHD of 16 mg/day risperidone based on mg/m^2 body surface area. When the offspring of pregnant rats, treated with risperidone at 0.6 times the MRHD based on mg/m^2 body surface area, reached adulthood, learning was impaired. Increased neuronal cell death occurred in the fetal brains of the offspring of pregnant rats treated at 0.5 to 1.2 times the MRHD; the postnatal development and growth of the offspring was delayed.

In rat reproduction studies with risperidone, pup deaths occurred at oral doses which are less than the MRHD of risperidone based on mg/m^2 body surface area; it is not known whether these deaths were due to a direct effect on the fetuses or pups or, to effects on the dams.

8.2 Lactation

Risk Summary

Limited data from published literature report the presence of paliperidone in human breast milk. There is no information on the effects on the breastfed infant, or the effects on milk production; however, there are reports of sedation, failure to thrive, jitteriness, and extrapyramidal symptoms (tremors and abnormal muscle movements) in breastfed infants exposed to paliperidone's parent compound, risperidone (see Clinical Considerations) . Paliperidone has been detected in plasma in adult subjects up to 18 months after a single-dose administration of 3-month paliperidone palmitate extended-release injectable suspension. The clinical significance on the breastfed infant is not known [see Clinical Pharmacology (12.3)] . The developmental and health benefits of breastfeeding should be considered along with the mother's clinical need for INVEGA HAFYERA and any potential adverse effects on the breastfed child from INVEGA HAFYERA or from the mother's underlying condition.

Clinical Considerations

Infants exposed to INVEGA HAFYERA through breastmilk should be monitored for excess sedation, failure to thrive, jitteriness, and extrapyramidal symptoms (tremors and abnormal muscle movements).

8.3 Females and Males of Reproductive Potential

Infertility

Females

Based on the pharmacologic action of paliperidone (D2 receptor antagonism), treatment with INVEGA HAFYERA may result in an increase in serum prolactin levels, which may lead to a reversible reduction in fertility in females of reproductive potential [see Warnings and Precautions (5.10)] .

8.4 Pediatric Use

Safety and effectiveness of INVEGA HAFYERA in patients less than 18 years of age have not been established. Use of INVEGA HAFYERA is not recommended in pediatric patients because of the potential longer duration of an adverse event. In clinical trials of oral paliperidone, there were notably higher incidences of dystonia, hyperkinesia, tremor, and parkinsonism in the adolescent population as compared to the adult studies.

Juvenile Animal Studies

No juvenile animal studies were conducted with the 6-month paliperidone palmitate extended-release injectable suspension.

In a study in which juvenile rats were treated with oral paliperidone from days 24 to 73 of age, a reversible impairment of performance in a test of learning and memory was seen, in females only, with a no-effect dose of 0.63 mg/kg/day, which produced plasma levels (AUC) of paliperidone similar to those in adolescents dosed at 12 mg/day. No other consistent effects on neurobehavioral or reproductive development were seen up to the highest dose tested (2.5 mg/kg/day), which produced plasma levels of paliperidone 2–3 times those in adolescents.

Juvenile dogs were treated for 40 weeks with oral risperidone, which is extensively metabolized to paliperidone in animals and humans, at doses of 0.31, 1.25, or 5 mg/kg/day. Decreased bone length and density were seen with a no-effect dose of 0.31 mg/kg/day, which produced plasma levels (AUC) of risperidone plus paliperidone which were similar to those in children and adolescents receiving the MRHD of risperidone. In addition, a delay in sexual maturation was seen at all doses in both males and females. The above effects showed little or no reversibility in females after a 12-week drug-free recovery period.

8.5 Geriatric Use

The clinical study of INVEGA HAFYERA did not include sufficient numbers of subjects aged 65 and over to determine whether they respond differently from younger subjects. Other reported clinical experience has not identified differences in responses between the elderly and younger patients.

This drug is substantially excreted by the kidney and clearance is decreased in patients with renal impairment [see Clinical Pharmacology (12.3)] . Because elderly patients are more likely to have decreased renal function, INVEGA HAFYERA is not recommended to be used in elderly patients with mild, moderate or severe renal impairment [see Use in Specific Populations (8.6)] .

8.6 Renal Impairment

Use of INVEGA HAFYERA is not recommended for use in patients with moderate or severe renal impairment (creatinine clearance <50 mL/min). Use of INVEGA HAFYERA in patients with mild renal impairment (creatinine clearance ≥50 mL/min to <80 mL/min) is based on the patient’s previous dose of PP1M or PP3M before transitioning to INVEGA HAFYERA [see Dosage and Administration (2.4) and Clinical Pharmacology (12.3)] .

8.7 Hepatic Impairment

INVEGA HAFYERA has not been studied in patients with hepatic impairment. Based on a study with oral paliperidone, no dose adjustment is required in patients with mild or moderate hepatic impairment. Paliperidone has not been studied in patients with severe hepatic impairment [see Clinical Pharmacology (12.3)] .

8.8 Patients with Parkinson's Disease or Lewy Body Dementia

Patients with Parkinson's Disease or Dementia with Lewy Bodies can experience increased sensitivity to INVEGA HAFYERA. Manifestations can include confusion, obtundation, postural instability with frequent falls, extrapyramidal symptoms, and clinical features consistent with neuroleptic malignant syndrome.

9 DRUG ABUSE AND DEPENDENCE

9.1 Controlled Substance

INVEGA HAFYERA contains paliperidone, which is not a controlled substance.

9.2 Abuse

Paliperidone has not been systematically studied in animals or humans for its potential for abuse.

9.3 Dependence

Paliperidone has not been systematically studied in animals or humans for its potential for tolerance or physical dependence.

10 OVERDOSAGE

Human Experience

No cases of overdose were reported in premarketing studies with paliperidone palmitate injection.

While experience with paliperidone overdose is limited, among the few cases of overdose reported in premarketing trials with oral paliperidone, the highest estimated ingestion was 405 mg. Observed signs and symptoms included extrapyramidal symptoms and gait unsteadiness. Other potential signs and symptoms include those resulting from an exaggeration of paliperidone's known pharmacological effects, i.e., drowsiness and sedation, tachycardia and hypotension, and QT prolongation. Torsades de pointes and ventricular fibrillation have been reported in a patient in the setting of overdose with oral paliperidone.

Paliperidone is the major active metabolite of risperidone. Refer to the OVERDOSAGE section of the risperidone prescribing information for overdose experience with risperidone.

Management of Overdosage

Contact a Certified Poison Control Center for the most up to date information on the management of paliperidone and INVEGA HAFYERA overdosage (1-800-222-1222 or www.poison.org). Provide supportive care, including close medical supervision and monitoring. Treatment should consist of general measures employed in the management of overdosage with any drug. Consider the possibility of multiple drug overdosage. Ensure an adequate airway, oxygenation, and ventilation. Monitor cardiac rhythm and vital signs. Use supportive and symptomatic measures. There is no specific antidote to paliperidone.

Consider the extended-release characteristics of INVEGA HAFYERA and the half-life of paliperidone when assessing treatment needs and recovery.

11 DESCRIPTION

INVEGA HAFYERA® contains a racemic mixture of (+)- and (-)- paliperidone palmitate. Paliperidone palmitate is an atypical antipsychotic belonging to the chemical class of benzisoxazole derivatives. The chemical name is (9 RS)-3-[2-[4-(6-Fluoro-1,2-benzisoxazol-3-yl)piperidin-1-yl]ethyl]-2-methyl-4-oxo-6,7,8,9-tetrahydro-4 H-pyrido[1,2- a]pyrimadin-9-yl hexadecanoate. Its molecular formula is C39H57FN4O4 and its molecular weight is 664.89. The structural formula is:

Paliperidone palmitate is very slightly soluble in ethanol and methanol, practically insoluble in polyethylene glycol 400 and propylene glycol, and slightly soluble in ethyl acetate.

INVEGA HAFYERA is available as a white to off-white sterile aqueous extended-release suspension for intramuscular injection in dose strengths of 1,092 mg and 1,560 mg paliperidone palmitate. The drug product hydrolyzes to the active moiety, paliperidone, resulting in dose strengths of 700 mg, and 1,000 mg of paliperidone, respectively. The inactive ingredients are polysorbate 20 (10 mg/mL), polyethylene glycol 4000 (75 mg/mL), citric acid monohydrate (7.5 mg/mL), sodium dihydrogen phosphate monohydrate (6 mg/mL), sodium hydroxide (5.4 mg/mL), and water for injection.

INVEGA HAFYERA is provided in a single-dose prefilled syringe (cyclic-olefin-copolymer) prefilled with either 700 mg (3.5 mL), or 1,000 mg (5.0 mL) paliperidone (as 1,092 mg, or 1,560 mg paliperidone palmitate) suspension with a tip cap, plunger rod, backstop and a thin walled 20G, 1½-inch safety needle.

12 CLINICAL PHARMACOLOGY

12.1 Mechanism of Action

Paliperidone palmitate is hydrolyzed to paliperidone [see Clinical Pharmacology (12.3)] . Paliperidone is the major active metabolite of risperidone. The mechanism of action of paliperidone is unclear. However, its efficacy in the treatment of schizophrenia could be mediated through a combination of central dopamine D2 and serotonin 5HT2A receptor antagonism.

12.2 Pharmacodynamics

In vitro, paliperidone acts as an antagonist at the central dopamine D2 and serotonin 5HT2A receptors with binding affinities (Ki values) of 1.6–2.8 nM and 0.8–1.2 nM, respectively. Paliperidone also acts as an antagonist at histamine H1 and α1 and α2 adrenergic receptors with binding affinities of 32 nM, 4 nM, and 17 nM, respectively. Paliperidone has no appreciable affinity for cholinergic muscarinic or β1- and β2-adrenergic receptors. The pharmacological activity of the (+)- and (-)- paliperidone enantiomers is qualitatively and quantitatively similar.

12.3 Pharmacokinetics

The pharmacokinetics for INVEGA HAFYERA presented below are based on gluteal administration only.

INVEGA HAFYERA delivers paliperidone over a 6-month period, compared to the 1-month or 3-month products which are administered every month or every three months, respectively. INVEGA HAFYERA doses of 1,092 mg and 1,560 mg result in paliperidone total exposure ranges that are encompassed within the exposure range for corresponding doses of 1-month paliperidone palmitate injections (PP1M) (156 mg and 234 mg) or corresponding doses of 3-month paliperidone palmitate (PP3M) injections (546 mg and 819 mg, respectively) or to corresponding once daily doses of paliperidone extended-release tablets. However, mean trough concentrations (Ctrough) at the end of the dosing interval were approximately 20 – 25% lower for INVEGA HAFYERA as compared to corresponding doses of 3-month paliperidone palmitate. The mean peak concentration (Cmax) was higher (1.4 to 1.5-fold) for INVEGA HAFYERA as compared to corresponding doses of 3-month paliperidone palmitate.

Inter-subject variability in paliperidone PK parameters for INVEGA HAFYERA ranged from 42 to 48% for AUC6months and ranged from 56 to 103% for Cmax. Because of the difference in pharmacokinetic profiles among the four paliperidone products, caution should be exercised when making a direct comparison of their pharmacokinetic properties.

Absorption

Due to its extremely low water solubility, the 6-month formulation of paliperidone palmitate dissolves slowly after intramuscular injection before being hydrolyzed to paliperidone and absorbed into the systemic circulation. The release of the drug starts as early as day 1 and is predicted to last longer than 18 months.

Following gluteal injection(s) of INVEGA HAFYERA at doses of 1,092 or 1,560 mg plasma concentrations of paliperidone rise to reach maximum concentrations at a median Tmax of 29 to 32 days. The release profile and dosing regimen of INVEGA HAFYERA results in sustained concentrations over 6 months. The total and peak dose-normalized exposures of paliperidone following INVEGA HAFYERA administration were comparable between 1,092 mg and 1,560 mg dose levels. The median steady-state peak:trough ratio for an INVEGA HAFYERA dose is 3.1 and 3.0 following gluteal administration of 1,092 and 1,560 mg respectively.

Distribution

Following administration of INVEGA HAFYERA, the apparent volume of distribution of paliperidone is 1,960 L.

The plasma protein binding of racemic paliperidone is 74%.

Elimination

Metabolism

In a study with oral immediate-release^14C-paliperidone, one week following administration of a single oral dose of 1 mg immediate-release^14C-paliperidone, 59% of the dose was excreted unchanged into urine, indicating that paliperidone is not extensively metabolized in the liver. Approximately 80% of the administered radioactivity was recovered in urine and 11% in the feces. Four metabolic pathways have been identified in vivo, none of which accounted for more than 10% of the dose: dealkylation, hydroxylation, dehydrogenation, and benzisoxazole scission. Although in vitro studies suggested a role for CYP2D6 and CYP3A4 in the metabolism of paliperidone, there is no evidence in vivo that these isozymes play a significant role in the metabolism of paliperidone. Population pharmacokinetics analyses indicated no discernible difference on the apparent clearance of paliperidone after administration of oral paliperidone between extensive metabolizers and poor metabolizers of CYP2D6 substrates.

Excretion

The median apparent half-life of paliperidone following a single INVEGA HAFYERA of either 1,092 or 1,560 mg was 148 and 159 days respectively. the concentration of paliperidone remaining in the circulation 18 months after dosing of 1,560 mg 6-month paliperidone palmitate extended-release injectable suspension stopped is estimated to be 18% of the average steady-state levels.

Drug Interaction Studies

No specific drug interaction studies have been performed with INVEGA HAFYERA. The information below is obtained from studies with oral paliperidone.

Effects of other drugs on the exposures of INVEGA HAFYERA are summarized in Figure 1. After oral administration of 20 mg/day of paroxetine (a potent CYP2D6 inhibitor), an increase in mean Cmax and AUC values at steady-state was observed (see Figure 1). Higher doses of paroxetine have not been studied. The clinical relevance is unknown. After oral administration of paliperidone, a decrease in mean Cmax and AUC values at steady state is expected when patients are treated with carbamazepine, a strong inducer of both CYP3A4 and P-gp [see Drug Interactions (7.1)] . This decrease is caused, to a substantial degree, by a 35% increase in renal clearance of paliperidone.

Figure 1: Effects of Other Drugs on INVEGA HAFYERA Pharmacokinetics

In vitro studies indicate that CYP2D6 and CYP3A4 may be involved in paliperidone metabolism, however, there is no evidence in vivo that inhibitors of these enzymes significantly affect the metabolism of paliperidone; they contribute to only a small fraction of total body clearance. In vitro studies demonstrated that paliperidone is a substrate of P-glycoprotein (P-gp) [see Drug Interactions (7.2)] .

Co-administration of a single dose of an oral paliperidone extended-release tablet 12 mg with divalproex sodium extended-release tablets (two 500 mg tablets once daily) resulted in an increase of approximately 50% in the Cmax and AUC of paliperidone. Since no significant effect on the systemic clearance was observed, a clinically significant interaction would not be expected between divalproex sodium extended-release tablets and INVEGA HAFYERA. This interaction has not been studied with INVEGA HAFYERA.

In vitro studies in human liver microsomes demonstrated that paliperidone does not substantially inhibit the metabolism of drugs metabolized by cytochrome P450 isozymes, including CYP1A2, CYP2A6, CYP2C8/9/10, CYP2D6, CYP2E1, CYP3A4, and CYP3A5. Therefore, paliperidone is not expected to inhibit clearance of drugs that are metabolized by these metabolic pathways in a clinically relevant manner. Paliperidone is also not expected to have enzyme inducing properties.

Paliperidone is a weak inhibitor of P-gp at high concentrations. No in vivo data are available, and the clinical relevance is unknown.

The effects of INVEGA HAFYERA on the exposures of other drugs are summarized in Figure 2.

After oral administration of paliperidone, the steady-state Cmax and AUC of valproate were not affected in 13 patients stabilized on valproate. In a clinical study, subjects on stable doses of valproate had comparable valproate average plasma concentrations when oral paliperidone extended-release tablets 3–15 mg/day was added to their existing valproate treatment [see Drug Interactions (7.1)] .

Figure 2: Effects of INVEGA HAFYERA on Pharmacokinetics of Other Drugs

Specific Populations

No specific pharmacokinetic studies have been performed with INVEGA HAFYERA in specific populations. All the information is obtained from studies with oral paliperidone or is based on the population pharmacokinetic modelling of oral paliperidone and INVEGA HAFYERA. Exposures of paliperidone in specific populations (renal impairment, hepatic impairment and elderly) are summarized in Figure 3 [see Dosage and Administration (2.5) and Use in Specific Populations (8.6)] .

Patients with Hepatic Impairment

After oral administration of paliperidone in patients with moderate hepatic impairment, the plasma concentrations of free paliperidone were similar to those of healthy subjects, although total paliperidone exposure decreased because of a decrease in protein binding. Paliperidone has not been studied in patients with severe hepatic impairment [see Use in Specific Populations (8.7)] .

Geriatric Patients

After oral administration of paliperidone in elderly subjects, the Cmax and AUC increased 1.2-fold compared to young subjects. This may be attributable to age-related decreases in creatinine clearance [see Dosage and Administration (2.5) and Use in Specific Populations (8.5)] .

Figure 3: Effects of Intrinsic factors on Paliperidone Pharmacokinetics

Smokers

Based on in vitro studies utilizing human liver enzymes, paliperidone is not a substrate for CYP1A2; smoking should, therefore, not have an effect on the pharmacokinetics of paliperidone.

Male and Female Patients

Slower absorption was observed in females in a population pharmacokinetic analysis. At apparent steady-state with 6-month paliperidone palmitate extended-release injectable suspension the trough concentrations were similar between males and females.

Obese Patients

Lower Cmax was observed in overweight and obese subjects. At apparent steady state with INVEGA HAFYERA, the trough concentrations were similar among normal, overweight, and obese subjects.

13 NONCLINICAL TOXICOLOGY

13.1 Carcinogenesis, Mutagenesis, Impairment of Fertility

Carcinogenesis

No carcinogenicity studies were conducted with the 6-month paliperidone palmitate extended-release injectable suspension.

The carcinogenic potential of intramuscularly injected 1-month paliperidone palmitate extended-release injectable suspension was assessed in rats. There was an increase in mammary gland adenocarcinomas in female rats at 16, 47, and 94 mg/kg/month, which are ~0.7, 2 and 4 times, respectively, the MRHD of 234 mg of the 1-month paliperidone palmitate extended-release suspension based on mg/m^2 body surface area. A no-effect dose was not established. Male rats showed an increase in mammary gland adenomas, fibroadenomas, and carcinomas at ~2 and 4 times the MRHD of 234 mg of the 1-month paliperidone palmitate extended-release suspension based on mg/m^2 body surface area. A carcinogenicity study in mice has not been conducted with paliperidone palmitate.

Carcinogenicity studies with risperidone, which is extensively converted to paliperidone in rats, mice, and humans, were conducted in Swiss albino mice and Wistar rats. Risperidone was administered in the diet at daily doses of 0.63, 2.5, and 10 mg/kg for 18 months to mice and for 25 months to rats. A maximum tolerated dose was not achieved in male mice. There were statistically significant increases in pituitary gland adenomas, endocrine pancreas adenomas, and mammary gland adenocarcinomas. The no-effect dose for these tumors was less than or equal to the maximum recommended human dose of risperidone based on mg/m^2body surface area (see risperidone package insert). An increase in mammary, pituitary, and endocrine pancreas neoplasms has been found in rodents after chronic administration of other antipsychotic drugs and is considered to be mediated by prolonged dopamine D2 antagonism and hyperprolactinemia. The relevance of these tumor findings in rodents to human risk is unclear [see Warnings and Precautions (5.10)] .

Mutagenesis

Paliperidone palmitate showed no genotoxicity in the in vitro Ames bacterial reverse mutation test or the mouse lymphoma assay. Paliperidone was not genotoxic in the in vitro Ames bacterial reverse mutation test, the mouse lymphoma assay or the in vivo rat bone marrow micronucleus test.

Impairment of Fertility

No fertility studies were conducted with the 6-month paliperidone palmitate extended-release injectable suspension.

In an oral paliperidone study of fertility, the percentage of treated female rats that became pregnant was not affected at oral doses of paliperidone of up to 2.5 mg/kg/day which is 2 times the oral MRHD of 12 mg based on mg/m^2 body surface area. However, pre- and post-implantation loss was increased, and the number of live embryos was slightly decreased, at 2.5 mg/kg, a dose that also caused slight maternal toxicity. These parameters were not affected at an oral dose of 0.63 mg/kg, which is half of the oral MRHD of 12 mg based on mg/m^2 body surface area.

The fertility of male rats was not affected at oral doses of paliperidone of up to 2 times the oral MRHD of 12 mg/day based on mg/m^2 body surface area, although sperm count and sperm viability studies were not conducted with paliperidone. In a subchronic study in Beagle dogs with risperidone, which is extensively converted to paliperidone in dogs and humans, all doses tested (0.31 mg/kg – 5.0 mg/kg) resulted in decreases in serum testosterone and in sperm motility and concentration (0.6 to 10 times the MRHD of 16 mg/day for risperidone, based on mg/m^2 body surface area). Serum testosterone and sperm parameters partially recovered, but remained decreased after the last observation (two months after treatment was discontinued).

13.2 Animal Toxicology and/or Pharmacology

Injection site toxicity was assessed in minipigs injected intramuscularly with the 6-month paliperidone palmitate extended-release injectable suspension at doses up to 2,115 mg, which is slightly above the MRHD. Injection site inflammatory reactions were greater and more advanced than reactions to the 1-month paliperidone palmitate extended-release injectable suspension. Reversibility of these findings was not examined.

14 CLINICAL STUDIES

The efficacy of INVEGA HAFYERA for the treatment of schizophrenia in patients who had previously been stably treated with either PP1M for at least 4 months or PP3M for at least one 3-month injection cycle was evaluated in a randomized, double-blind, active-controlled, interventional, parallel-group, multicenter, non-inferiority study designed to evaluate time to relapse in adults with a DSM-5 diagnosis of schizophrenia.

Patients could enter the study if previously treated with PP1M at dosages of 156 or 234 mg, PP3M at dosages of 546 or 819 mg, injectable risperidone at dosages of 50 mg, or any oral antipsychotic with a reason to change (e.g., efficacy, safety, tolerability, or a preference for a long-acting injectable medication) and with a PANSS total score of <70 points.

After establishing tolerability with PP1M (at dosages of 156 or 234 mg) or PP3M (at dosages of 546 or 819 mg) and clinical stability, defined by having a PANSS total score of <70 points for the previous 2 assessments prior to the double-blind phase, patients were randomized in a 2:1 ratio to receive INVEGA HAFYERA (478 patients) or PP3M (224 patients).

The primary efficacy variable was time to first relapse in the double-blind phase. The primary efficacy analysis was based on the difference in Kaplan-Meier 12-month estimates of percentage of subjects remaining relapse-free between INVEGA HAFYERA and 3-month paliperidone palmitate extended-release injectable suspension. Relapse was pre-defined as emergence of one or more of the following: psychiatric hospitalization, ≥25% increase (if the baseline score was >40) or a 10-point increase (if the baseline score was ≤40) in total PANSS score on two consecutive assessments, deliberate self-injury, violent behavior, suicidal/homicidal ideation: a score of ≥5 (if the maximum baseline score was ≤3) or ≥6 (if the maximum baseline score was 4) on two consecutive assessments of the specific PANSS items.

A relapse event was experienced by 7.5% and 4.9% of patients in the INVEGA HAFYERA and PP3M treatment groups, respectively, with the Kaplan-Meier estimated difference (INVEGA HAFYERA – PP3M) of 2.9% (95% CI: -1.1 to 6.8). The upper bound of the 95% CI (6.8%) was less than 10%, the prespecified non-inferiority margin. The study demonstrated non-inferiority of INVEGA HAFYERA to PP3M. A Kaplan-Meier plot of time to relapse by treatment group is shown in Figure 4.

Figure 4: Kaplan-Meier Plot of Cumulative Proportion of Patients with Relapse Over Time

An evaluation of population subgroups did not reveal any clinically significant differences in responsiveness on the basis of gender, age, or race.

16 HOW SUPPLIED/STORAGE AND HANDLING

INVEGA HAFYERA® is available as a white to off-white sterile aqueous extended-release suspension for gluteal intramuscular injection in dose strengths of 1,092 mg/3.5 mL and 1,560 mg/5 mL paliperidone palmitate. The kit contains a single-dose prefilled syringe and a 20G, 1½-inch safety needle.

1,092 mg paliperidone palmitate kit (NDC 50458-611-01)

1,560 mg paliperidone palmitate kit (NDC 50458-612-01)

Storage and Handling

Store at room temperature 20 °C to 25 °C (68 °F to 77 °F); excursions between 15 °C and 30 °C (59 °F and 86 °F) are permitted. Do not mix with any other product or diluent.

Ship and store in a horizontal position. See arrows on product carton for proper orientation.

17 PATIENT COUNSELING INFORMATION

Advise the patient to read the FDA-approved patient labeling (Patient Information).

Neuroleptic Malignant Syndrome (NMS)

Counsel patients about a potentially fatal side effect referred to as Neuroleptic Malignant Syndrome (NMS) that has been reported in association with administration of antipsychotic drugs. Patients should contact their health care provider or report to the emergency room if they experience the following signs and symptoms of NMS, including hyperpyrexia, muscle rigidity, altered mental status, and evidence of autonomic instability (irregular pulse or blood pressure, tachycardia, diaphoresis, and cardiac dysrhythmia [see Warnings and Precautions (5.3)] .

Tardive Dyskinesia

Counsel patients on the signs and symptoms of tardive dyskinesia and to contact their health care provider if these abnormal movements occur [see Warnings and Precautions (5.5)] .

Metabolic Changes

Educate patients about the risk of metabolic changes, how to recognize symptoms of hyperglycemia (high blood sugar) and diabetes mellitus (e.g., polydipsia, polyuria, polyphagia, and weakness), and the need for specific monitoring, including blood glucose, lipids, and weight [see Warnings and Precautions (5.6)] .

Orthostatic Hypotension

Educate patients about the risk of orthostatic hypotension, particularly at the time of initiating treatment, re-initiating treatment, or increasing the dose [see Warnings and Precautions (5.7)] .

Leukopenia/Neutropenia

Advise patients with a pre-existing low WBC or a history of drug induced leukopenia/neutropenia they should have their CBC monitored while taking INVEGA HAFYERA [see Warnings and Precautions (5.9)] .

Hyperprolactinemia

Counsel patients on signs and symptoms of hyperprolactinemia that may be associated with chronic use of INVEGA HAFYERA. Advise them to seek medical attention if they experience any of the following: amenorrhea or galactorrhea in females, erectile dysfunction or gynecomastia in males. [See Warnings and Precautions (5.10)].

Interference with Cognitive and Motor Performance

As INVEGA HAFYERA has the potential to impair judgment, thinking, or motor skills, caution patients about operating hazardous machinery, including automobiles, until they are reasonably certain that INVEGA HAFYERA therapy does not affect them adversely [see Warnings and Precautions (5.11)] .

Priapism

Advise patients of the possibility of painful or prolonged penile erections (priapism). Instruct the patient to seek immediate medical attention in the event of priapism [see Warnings and Precautions (5.14)] .

Heat Exposure and Dehydration

Counsel patients on the importance of avoiding overheating and dehydration [see Warnings and Precautions (5.15)] .

Concomitant Medication

Advise patients to inform their health care providers if they are taking, or plan to take any prescription or over-the-counter drugs, as there is a potential for interactions [see Drug Interactions (7)] .

Pregnancy

Advise patients to notify their healthcare provider if they become pregnant or intend to become pregnant during treatment with INVEGA HAFYERA. Advise patients that INVEGA HAFYERA may cause extrapyramidal and/or withdrawal symptoms in a neonate. Advise patients that there is a pregnancy registry that monitors pregnancy outcomes in women exposed to INVEGA HAFYERA during pregnancy [see Use in Specific Populations (8.1)] .

Lactation

Advise breastfeeding women using INVEGA HAFYERA to monitor infants for somnolence, failure to thrive, jitteriness, and extrapyramidal symptoms (tremors and abnormal muscle movements) and to seek medical care if they notice these signs [see Use in Specific Populations (8.2)] .

Infertility

Advise females of reproductive potential that INVEGA HAFYERA may impair fertility due to an increase in serum prolactin levels. The effects on fertility are reversible [see Use in Specific Populations (8.3)] .

INVEGA HAFYERA (paliperidone palmitate) Extended-Release Injectable Suspension

IINVEGA TRINZA, INVEGA SUSTENNA, RISPERDAL, and RISPERDAL CONSTA are trademarks of Janssen Pharmaceuticals, Inc.

Manufactured for:
Janssen Pharmaceuticals, Inc.
Titusville, NJ 08560, USA

For patent information: www.janssenpatents.com

© Johnson & Johnson and its affiliates 2021

PATIENT INFORMATION
INVEGA HAFYERA ® (in-VAY-guh HAF-ye-RA)
(paliperidone palmitate)
extended-release injectable suspension

What is the most important information I should know about INVEGA HAFYERA?
INVEGA HAFYERA may cause serious side effects, including:

- Increased risk of death in elderly people with dementia-related psychosis. INVEGA HAFYERA increases the risk of death in elderly people who have lost touch with reality (psychosis) due to confusion and memory loss (dementia). INVEGA HAFYERA is not for the treatment of people with dementia-related psychosis.

What is INVEGA HAFYERA?
INVEGA HAFYERA is a prescription medicine given by injection by a healthcare provider 1 time every 6 months and used for the treatment of schizophrenia in adults who have been adequately treated with either:

- A 1 time each month paliperidone palmitate extended-release injectable suspension for at least 4 months.
- A 1 time every 3 months paliperidone palmitate extended-release injectable suspension for at least 3 months.

It is not known if INVEGA HAFYERA is safe and effective in children under 18 years of age.

Do not receive INVEGA HAFYERA if you are allergic to paliperidone palmitate, risperidone, or any of the ingredients in INVEGA HAFYERA. See the end of this Patient Information leaflet for a complete list of ingredients in INVEGA HAFYERA.

Before receiving INVEGA HAFYERA, tell your healthcare provider about all your medical conditions, including if you:

- have had Neuroleptic Malignant Syndrome (NMS)
- have or have had heart problems, including a heart attack, heart failure, abnormal heart rhythm, or long QT syndrome
- have or have had low levels of potassium or magnesium in your blood
- have or have had uncontrolled movements of your tongue, face, mouth, or jaw (tardive dyskinesia)
- have or have had kidney or liver problems
- have diabetes or have a family history of diabetes
- have Parkinson's disease or a type of dementia called Lewy Body Dementia
- have had a low white blood cell count
- have had problems with dizziness or fainting or are being treated for high blood pressure
- have or have had seizures or epilepsy
- are pregnant or plan to become pregnant. It is not known if INVEGA HAFYERA will harm your unborn baby.
  - Tell your healthcare provider right away if you become pregnant or think you may be pregnant during treatment with INVEGA HAFYERA.
  - If you become pregnant while receiving INVEGA HAFYERA, talk to your healthcare provider about registering with the National Pregnancy Registry for Atypical Antipsychotics. You can register by calling 1-866-961-2388 or visit http://womensmentalhealth.org/clinical-and-research-programs/pregnancyregistry/.
  - Babies born to mothers who receive INVEGA HAFYERA during their third trimester of pregnancy may develop agitation, low muscle tone (floppy baby syndrome) tremors, excessive sleepiness, breathing problems, and feeding problems. Tell your healthcare provider right away if your baby develops any of these symptoms.
- are breastfeeding or plan to breastfeed. INVEGA HAFYERA can pass into your breast milk. Talk to your healthcare provider about the best way to feed your baby during treatment with INVEGA HAFYERA.

Tell your healthcare provider about all the medicines you take, including prescription and over-the-counter medicines, vitamins, and herbal supplements.
INVEGA HAFYERA and other medicines may affect each other causing possible serious side effects. INVEGA HAFYERA may affect the way other medicines work, and other medicines may affect how INVEGA HAFYERA works.
Your healthcare provider can tell you if it is safe to receive INVEGA HAFYERA with your other medicines. Do not start or stop any medicines during treatment with INVEGA HAFYERA without talking to your healthcare provider first.
Know the medicines you take. Keep a list of them to show to your healthcare provider or pharmacist when you get a new medicine.

How will I receive INVEGA HAFYERA?

- Follow your INVEGA HAFYERA treatment schedule exactly as your healthcare provider tells you to.
- Your healthcare provider will tell you how much INVEGA HAFYERA you will receive and when you will receive it.
- INVEGA HAFYERA is given as an injection by your healthcare provider into the muscle (intramuscularly) of your buttocks, 1 time every 6 months.

What should I avoid while receiving INVEGA HAFYERA?

- Do not drive, operate heavy machinery, or do other dangerous activities until you know how INVEGA HAFYERA affects you. INVEGA HAFYERA may affect your judgment, thinking, or motor skills.
- Avoid getting too hot or dehydrated.
  - Do not exercise too much.
  - In hot weather, stay inside in a cool place if possible.
  - Stay out of the sun.
  - Do not wear too much clothing or heavy clothing.
  - Drink plenty of water.

What are the possible side effects of INVEGA HAFYERA?
INVEGA HAFYERA may cause serious side effects, including:

- See " What is the most important information I should know about INVEGA HAFYERA?"
- Cerebrovascular problems (including stroke) in elderly people with dementia-related psychosis that can lead to death.
- Neuroleptic Malignant Syndrome (NMS), a serious condition that can lead to death. Call your healthcare provider or go to your nearest hospital emergency room right away if you have some or all of the following signs and symptoms of NMS:

- high fever
- confusion
- changes in your breathing, pulse, heart rate, and blood pressure

- stiff muscles
- sweating

- Problems with your heartbeat.These heart problems can cause death. Call your healthcare provider right away if you have any of these symptoms:
  - passing out or feeling like you will pass out
  - dizziness
  - feeling as if your heart is pounding or missing beats
- Uncontrolled body movements (tardive dyskinesia). INVEGA HAFYERA may cause movements that you cannot control in your face, tongue, or other body parts. Tardive dyskinesia may not go away, even if you stop receiving INVEGA HAFYERA. Tardive dyskinesia may also start after you stop receiving INVEGA HAFYERA.
- Problems with your metabolism such as:
  - high blood sugar (hyperglycemia) and diabetes. Increases in blood sugar can happen in some people who receive INVEGA HAFYERA. Extremely high blood sugar can lead to coma or death. Your healthcare provider should check your blood sugar before you start and regularly during treatment with INVEGA HAFYERA.
    Call your healthcare provider if you have any of these symptoms of high blood sugar during treatment with INVEGA HAFYERA:

- feel very thirsty
- feel very hungry
- feel sick to your stomach

- need to urinate more than usual
- feel weak or tired
- feel confused, or your breath smells fruity

- increased fat levels (cholesterol and triglycerides) in your blood. Your healthcare provider should check the fat levels in your blood before you start and regularly during treatment with INVEGA HAFYERA.
- weight gain. You and your healthcare provider should check your weight before you start and often during treatment with INVEGA HAFYERA.

- Decreased blood pressure (orthostatic hypotension) and fainting.You may feel lightheaded or faint when you rise too quickly from a sitting or lying position, especially early in treatment or when the dose is changed.
- Falls. INVEGA HAFYERA may make you sleepy or dizzy, may cause a decrease in your blood pressure when changing position (orthostatic hypotension), and can slow your thinking and motor skills which may lead to falls that can cause fractures or other injuries.
- Low white blood cell count. Your healthcare provider may do blood tests during the first few months of treatment with INVEGA HAFYERA.
- Increased prolactin levels in your blood (hyperprolactinemia). INVEGA HAFYERA may cause a rise in the blood levels of a hormone called prolactin (hyperprolactinemia) that may cause side effects including missed menstrual periods, a reversible reduction in fertility in females who are able to become pregnant, leakage of milk from the breasts, development of breasts in men, or problems with erection.
- INVEGA HAFYERA can make you sleepy or dizzy, and can slow your thinking and motor skills. Do not drive, operate heavy machinery, or do other dangerous activities until you know how INVEGA HAFYERA affects you.
- Seizures (convulsions).
- Difficulty swallowing that can cause food or liquid to get into your lungs.
- Prolonged or painful erection lasting more than 4 hours (priapism). Call your healthcare provider or go to your nearest emergency room right away if you have an erection that lasts more than 4 hours.
- Problems controlling your body temperature so that you feel too warm. See, " What should I avoid while receiving INVEGA HAFYERA?"

The most common side effects of INVEGA HAFYERA include:

- upper respiratory tract infections
- weight gain
- feeling restlessness or difficulty sitting still
- tremors
- shuffling walk

- injection site reactions
- headache
- slow movements
- stiffness

These are not all the possible side effects of INVEGA HAFYERA.
Call your doctor for medical advice about side effects. You may report side effects to FDA at 1-800-FDA-1088.

General information about INVEGA HAFYERA.
Medicines are sometimes prescribed for purposes other than those listed in a Patient Information leaflet. You can ask your pharmacist or healthcare provider for information about INVEGA HAFYERA that is written for health professionals.

What are the ingredients in INVEGA HAFYERA?
Active ingredient: paliperidone palmitate
Inactive ingredients: polysorbate 20, polyethylene glycol 4000, citric acid monohydrate, sodium dihydrogen phosphate monohydrate, sodium hydroxide, and water for injection
Manufactured for: Janssen Pharmaceuticals, Inc., Titusville, NJ 08560, USA
For patent information: www.janssenpatents.com
© Johnson & Johnson and its affiliates 2021
For more information, go to www.invegahafyerahcp.com or call 1-800-526-7736.

This Patient Information has been approved by the U.S. Food and Drug Administration.

Revised: January 2025

INSTRUCTIONS FOR USE

INVEGA HAFYERA®
in-VAY-guh HAF-ye-RA
(paliperidone palmitate)
extended-release injectable suspension
For Gluteal Intramuscular
Injection Only

Administer every 6 months

Shake syringe with the syringe tip cap pointing up VERY FAST for at least 15 seconds, rest briefly, then shake again for 15 seconds

Important

Shipping and storing the carton in a horizontal orientation improves the ability to resuspend this highly concentrated product.

INVEGA HAFYERA must be administered by a healthcare professional as a single injection.
Do not divide dose into multiple injections.
INVEGA HAFYERA is intended for gluteal intramuscular use only. Inject slowly, deep into the muscle taking care to avoid injection into a blood vessel.

Dosing

Administer INVEGA HAFYERA once every 6 months.

Thin Wall Safety Needle

Thin wall safety needle is designed to be used with INVEGA HAFYERA. Therefore, it is important to only use the needle provided in the INVEGA HAFYERA suspension kit.

Dose pack contents

1. Prepare for the injection: this highly concentrated product requires specific steps to resuspend

Hold syringe with the tip cap pointing up

Shake syringe VERY FAST for at least 15 seconds, rest briefly, then shake again for 15 seconds
To ensure complete resuspension shake syringe with:

- Short, VERY FAST up and down motion
- Loose wrist

Proceed to the next step immediately after shaking.

Check suspension for solid product

- Uniform, thick and milky white
- It is normal to see air bubbles

- Solid product on sides and top of syringe
- Uneven mix
- Thin liquid

Product may clog. Shake syringe with the syringe tip cap pointing up VERY FAST for at least 15 seconds, rest, then shake again for 15 seconds.

Open needle pouch
Peel off the pouch cover.
Place pouch with the needle inside on a clean surface.

Remove syringe tip cap and attach needle
Hold the syringe with the tip cap pointing up.
Twist and pull off the cap.
Attach the safety needle to the syringe using a gentle twisting motion to avoid needle hub cracks or damage. Always check for signs of damage or leakage prior to administration.

Pull back plunger
Hold the syringe upright.
Gently pull back the plunger to clear the syringe tip of any solid product. This will make pressing the plunger easier during the injection.
Remove air bubbles
Press the plunger carefully until a drop of liquid comes out of the needle tip.

1. Slowly inject entire content and confirm

Select and clean a gluteal injection site
Wipe the gluteal site with an alcohol swab and allow it to dry.
Do not touch, fan or blow on the injection site after you have cleaned it.

Remove needle sheath
Pull the needle sheath away from the needle in a straight motion.
Do not twist the sheath, as this may loosen the needle from the syringe.

Slowly inject and confirm
Use slow, firm, consistent pressure to press the plunger completely. This should take approximately 30 seconds.
Continue to press the plunger if you feel resistance. This is normal.
While the needle is in the gluteal muscle, confirm that the entire content of the syringe has been injected.
Remove needle from the muscle.

1. After the injection

Secure needle
After the injection is complete, use your thumb or a flat surface to secure the needle in the safety device.
The needle is secure when you hear a "click" sound.

Dispose of properly and check injection site
Dispose of the syringe in an approved sharps container.
There may be a small amount of blood or liquid at the injection site. Hold pressure over the skin with a cotton ball or gauze pad until any bleeding stops.
Do not rub the injection site.
If needed, cover injection site with a bandage.

Manufactured for:

Janssen Pharmaceuticals, Inc.
Titusville, NJ 08560, USA

For patent information: www.janssenpatents.com

© Johnson & Johnson and its affiliates 2021

This Instructions for Use has been approved by the U.S. Food and Drug Administration. Revised: 2/2025

PRINCIPAL DISPLAY PANEL - 3.5 mL Syringe Carton

NDC 50458-611-01

Single-dose prefilled syringe. Use entire contents of syringe.

INVEGA HAFYERA™
(paliperidone palmitate)
extended-release injectable suspension

FOR GLUTEAL INTRAMUSCULAR INJECTION ONLY

Each injection must be administered only by
a healthcare professional.

Shake before using.

CONTENTS: 1 single-dose prefilled syringe and
1 needle (a 20G,1.5-inch thin wall safety needle).

Recommended Dosage: See Prescribing Information.

Rx only

Store at room temperature 20°C to 25°C
(68°F to 77°F); excursions between
15°C and 30°C (59°F and 86°F) are permitted.

SHIP AND STORE
THIS SIDE UP
LAY
FLAT

1,092 mg/3.5 mL

Each single-dose prefilled syringe contains
1,092 mg paliperidone palmitate.

6
MONTHS

Administer
every 6 months

Shake syringe
with the syringe
tip cap pointing
up VERY FAST
for at least
15 seconds, rest
briefly, then
shake again for
15 seconds

PRINCIPAL DISPLAY PANEL - 5 mL Syringe Carton

NDC 50458-612-01

Single-dose prefilled syringe. Use entire contents of syringe.

INVEGA HAFYERA™
(paliperidone palmitate)
extended-release injectable suspension

FOR GLUTEAL INTRAMUSCULAR INJECTION ONLY

Each injection must be administered only by
a healthcare professional.

Shake before using.

CONTENTS: 1 single-dose prefilled syringe and
1 needle (a 20G,1.5-inch thin wall safety needle).

Recommended Dosage: See Prescribing Information.

Rx only

Store at room temperature 20°C to 25°C
(68°F to 77°F); excursions between
15°C and 30°C (59°F and 86°F) are permitted.

SHIP AND STORE
THIS SIDE UP
LAY
FLAT

1,560 mg/5 mL

Each single-dose prefilled syringe contains
1,560 mg paliperidone palmitate.

6
MONTHS

Administer
every 6 months

Shake syringe
with the syringe
tip cap pointing
up VERY FAST
for at least
15 seconds, rest
briefly, then
shake again for
15 seconds